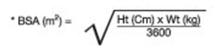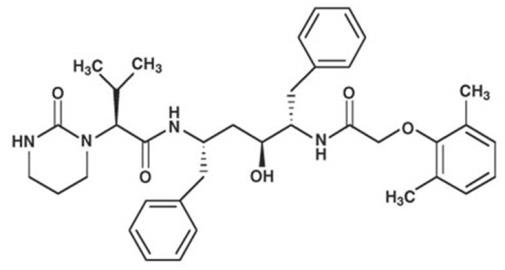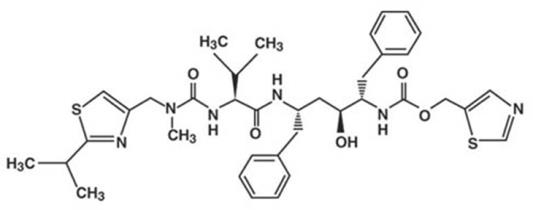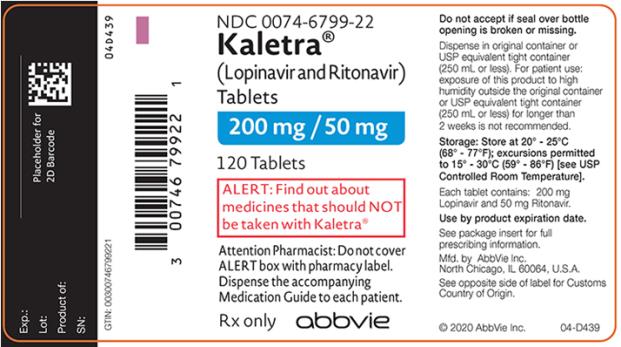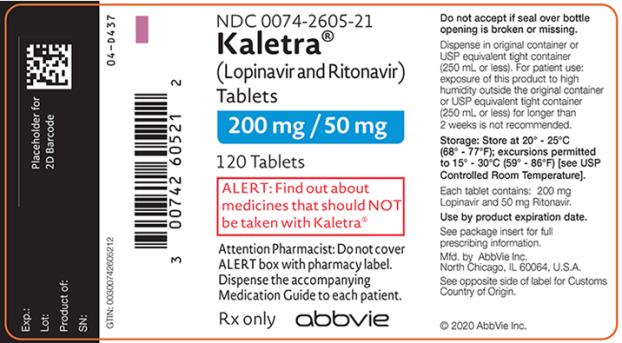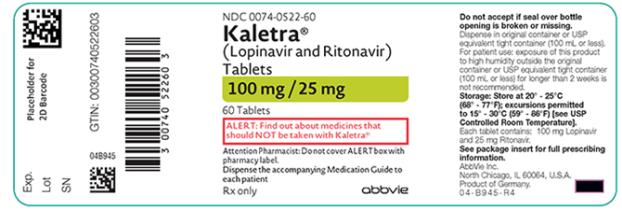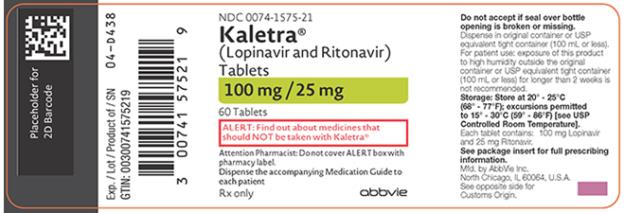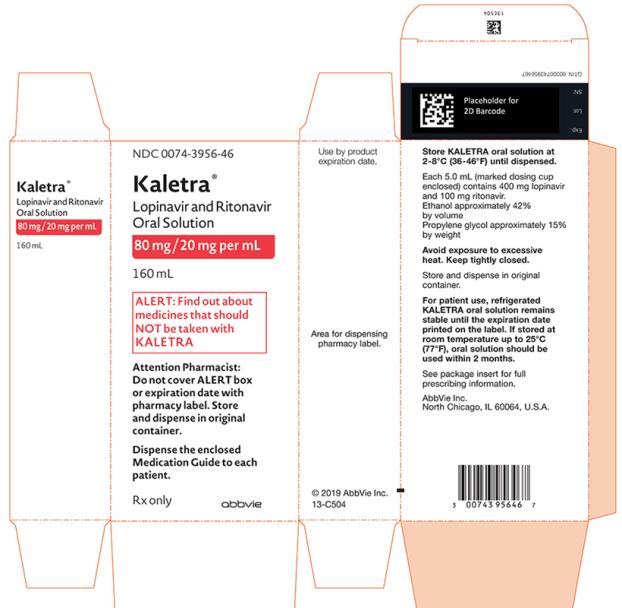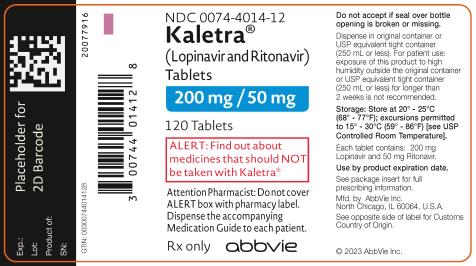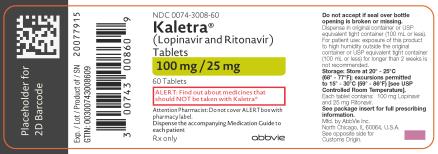 DRUG LABEL: Kaletra
NDC: 0074-0522 | Form: TABLET, FILM COATED
Manufacturer: AbbVie Inc.
Category: prescription | Type: HUMAN PRESCRIPTION DRUG LABEL
Date: 20230401

ACTIVE INGREDIENTS: LOPINAVIR 100 mg/1 1; RITONAVIR 25 mg/1 1
INACTIVE INGREDIENTS: SORBITAN MONOLAURATE; SODIUM STEARYL FUMARATE; TITANIUM DIOXIDE; TALC; POLYETHYLENE GLYCOL 3350; FERRIC OXIDE YELLOW; COPOVIDONE K25-31; SILICON DIOXIDE; POLYVINYL ALCOHOL, UNSPECIFIED

HIGHLIGHTS OF PRESCRIBING INFORMATION

These highlights do not include all the information needed to use KALETRA safely and effectively. See full prescribing information for KALETRA.
KALETRA (lopinavir and ritonavir) tablet, for oral use
KALETRA (lopinavir and ritonavir) oral solution
Initial U.S. Approval: 2000

RECENT MAJOR CHANGES

Contraindications (4) | 12/2019

1 INDICATIONS AND USAGE

KALETRA is an HIV-1 protease inhibitor indicated in combination with other antiretroviral agents for the treatment of HIV-1 infection in adults and pediatric patients (14 days and older). (1)

2 DOSAGE AND ADMINISTRATION

Tablets: May be taken with or without food, swallowed whole and not chewed, broken, or crushed. (2.1)

Oral solution: must be taken with food. (2.1)

KALETRA oral solution is not recommended for use with polyurethane feeding tubes due to potential incompatibility. Feeding tubes composed of silicone or polyvinyl chloride (PVC) can be used. (2.2)

Adults (2.3):

- Total recommended daily dosage is 800/200 mg given once or twice daily.
- KALETRA can be given as once daily or twice daily regimen. See Full Prescribing Information for details.
- KALETRA once daily dosing regimen is not recommended in:
  • Adult patients with three or more of the following lopinavir resistance-associated substitutions: L10F/I/R/V, K20M/N/R, L24I, L33F, M36I, I47V, G48V, I54L/T/V, V82A/C/F/S/T, and I84V. (12.4)
  • In combination with carbamazepine, phenobarbital, or phenytoin. (7.3)
  • In combination with efavirenz, nevirapine, or nelfinavir. (12.3)
  • In pregnant women. (2.5, 8.1, 12.3)

Pediatric Patients (14 days and older) (2.4):

- KALETRA once daily dosing regimen is not recommended in pediatric patients.
- Twice daily dose is based on body weight or body surface area.

Concomitant Therapy in Adults and Pediatric Patients:

- Dose adjustments of KALETRA may be needed when co-administering with efavirenz, nevirapine, or nelfinavir. (2.3, 2.4, 7.3)
- KALETRA oral solution should not be administered to neonates before a postmenstrual age (first day of the mother’s last menstrual period to birth plus the time elapsed after birth) of 42 weeks and a postnatal age of at least 14 days has been attained (2.4, 5.2)

Pregnancy (2.5):

- 400/100 mg twice daily in pregnant patients with no documented lopinavir-associated resistance substitutions.
- There are insufficient data to recommend a KALETRA dose for pregnant patients with any documented KALETRA-associated resistance substitutions.
- No dose adjustment of KALETRA is required for patients during the postpartum period.

3 DOSAGE FORMS AND STRENGTHS

- Tablets: 200 mg lopinavir and 50 mg ritonavir (3)
- Tablets: 100 mg lopinavir and 25 mg ritonavir (3)
- Oral solution: 80 mg lopinavir and 20 mg ritonavir per milliliter (3)

4 CONTRAINDICATIONS

- Hypersensitivity to KALETRA (e.g., toxic epidermal necrolysis, Stevens-Johnson syndrome, erythema multiforme, urticaria, angioedema) or any of its ingredients, including ritonavir. (4)
- Co-administration with drugs highly dependent on CYP3A for clearance and for which elevated plasma levels may result in serious and/or life-threatening events. (4)
- Co-administration with potent CYP3A inducers where significantly reduced lopinavir plasma concentrations may be associated with the potential for loss of virologic response and possible resistance and cross resistance. (4)

5 WARNINGS AND PRECAUTIONS

The following have been observed in patients receiving KALETRA:

- The concomitant use of KALETRA and certain other drugs may result in known or potentially significant drug interactions. Consult the full prescribing information prior to and during treatment for potential drug interactions. (5.1, 7.3)
- Toxicity in preterm neonates: KALETRA oral solution should not be used in preterm neonates in the immediate postnatal period because of possible toxicities. A safe and effective dose of KALETRA oral solution in this patient population has not been established. (2.4, 5.2)
- Pancreatitis: Fatalities have occurred; suspend therapy as clinically appropriate. (5.3)
- Hepatotoxicity: Fatalities have occurred. Monitor liver function before and during therapy, especially in patients with underlying hepatic disease, including hepatitis B and hepatitis C, or marked transaminase elevations. (5.4, 8.6)
- QT interval prolongation and isolated cases of torsade de pointes have been reported although causality could not be established. Avoid use in patients with congenital long QT syndrome, those with hypokalemia, and with other drugs that prolong the QT interval. (5.1, 5.5, 12.3)
- PR interval prolongation may occur in some patients. Cases of second and third degree heart block have been reported. Use with caution in patients with pre-existing conduction system disease, ischemic heart disease, cardiomyopathy, underlying structural heart disease or when administering with other drugs that may prolong the PR interval. (5.1, 5.6, 12.3)
- Patients may develop new onset or exacerbations of diabetes mellitus, hyperglycemia (5.7), immune reconstitution syndrome. (5.8), redistribution/accumulation of body fat. (5.10)
- Total cholesterol and triglycerides elevations. Monitor prior to therapy and periodically thereafter. (5.9)
- Hemophilia: Spontaneous bleeding may occur, and additional factor VIII may be required. (5.11)

6 ADVERSE REACTIONS

Commonly reported adverse reactions to KALETRA included diarrhea, nausea, vomiting, hypertriglyceridemia and hypercholesterolemia. (6.1)

To report SUSPECTED ADVERSE REACTIONS, contact AbbVie Inc. at 1-800-633-9110 or FDA at 1-800-FDA-1088 or www.fda.gov/medwatch

7 DRUG INTERACTIONS

Co-administration of KALETRA can alter the plasma concentrations of other drugs and other drugs may alter the plasma concentrations of lopinavir. The potential for drug-drug interactions must be considered prior to and during therapy. (4, 5.1, 7, 12.3)

8 USE IN SPECIFIC POPULATIONS

Lactation: Breastfeeding not recommended. (8.2)

FULL PRESCRIBING INFORMATION

1 INDICATIONS AND USAGE

KALETRA is indicated in combination with other antiretroviral agents for the treatment of HIV-1 infection in adults and pediatric patients 14 days and older.

Limitations of Use:

- Genotypic or phenotypic testing and/or treatment history should guide the use of KALETRA. The number of baseline lopinavir resistance-associated substitutions affects the virologic response to KALETRA [see Microbiology (12.4)].

2 DOSAGE AND ADMINISTRATION

2.1 General Administration Recommendations

KALETRA tablets may be taken with or without food. The tablets should be swallowed whole and not chewed, broken, or crushed. KALETRA oral solution must be taken with food.

2.2 Administering Oral Solution by Feeding Tube

Because KALETRA oral solution contains ethanol and propylene glycol, it is not recommended for use with polyurethane feeding tubes due to potential incompatibility. Feeding tubes that are compatible with ethanol and propylene glycol, such as silicone and polyvinyl chloride (PVC) feeding tubes, can be used for administration of KALETRA oral solution. Follow instructions for use of the feeding tube to administer the medicine.

2.3 Dosage Recommendations in Adults

KALETRA can be given in once daily or twice daily dosing regimen at dosages noted in Tables 1 and 2. KALETRA once daily dosing regimen is not recommended in:

- Adult patients with three or more of the following lopinavir resistance-associated substitutions: L10F/I/R/V, K20M/N/R, L24I, L33F, M36I, I47V, G48V, I54L/T/V, V82A/C/F/S/T, and I84V [see Microbiology (12.4)].
- In combination with carbamazepine, phenobarbital, or phenytoin [see Drug Interactions (7.3)].
- In combination with efavirenz, nevirapine, or nelfinavir [see Drug Interactions (7.3) and Clinical Pharmacology (12.3)].
- In pediatric patients younger than 18 years of age [see Dosage and Administration (2.4)].
- In pregnant women [see Dosage and Administration (2.5), Use in Specific Populations (8.1) and Clinical Pharmacology (12.3)].

Table 1. Recommended Dosage in Adults - KALETRA Once Daily Regimen

KALETRA Dosage Form | Recommended Dosage
200 mg/50 mg Tablets | 800 mg/200 mg (4 tablets) once daily
80 mg/20 mg per mL Oral Solution | 800 mg/200 mg (10 mL) once daily

Table 2. Recommended Dosage in Adults - KALETRA Twice Daily Regimen

KALETRA Dosage Form | Recommended Dosage
200 mg/50 mg Tablets | 400 mg/100 mg (2 tablets) twice daily
80 mg/20 mg per mL Oral Solution | 400 mg/100 mg (5 mL) twice daily

The dose of KALETRA must be increased when administered in combination with efavirenz, nevirapine or nelfinavir. Table 3 outlines the dosage recommendations for twice daily dosing when KALETRA is taken in combination with these agents.

Table 3. Recommended Dosage in Adults - KALETRA Twice Daily Regimen in Combination with Efavirenz, Nevirapine, or Nelfinavir

KALETRA Dosage Form | Recommended Dosage
200 mg/50 mg Tablets and 100 mg/25 mg Tablets | 500 mg/125 mg (2 tablets of 200 mg/50 mg + 1 tablet of 100 mg/25 mg) twice daily
80 mg/20 mg per mL Oral Solution | 520 mg/130 mg (6.5 mL) twice daily

2.4 Dosage Recommendations in Pediatric Patients

KALETRA tablets and oral solution are not recommended for once daily dosing in pediatric patients younger than 18 years of age. The dose of the oral solution should be administered using the calibrated cup (supplied) or oral dosing syringe. KALETRA 100/25 mg tablets should be considered only in children who have reliably demonstrated the ability to swallow the intact tablet.

KALETRA oral solution is not recommended in neonates before a postmenstrual age (first day of the mother’s last menstrual period to birth plus the time elapsed after birth) of 42 weeks and a postnatal age of at least 14 days has been attained [see Warnings and Precautions (5.2)].

KALETRA oral solution contains approximately 42% (v/v) ethanol and approximately 15% (w/v) propylene glycol. Total amounts of ethanol and propylene glycol from all medicines that are to be given to pediatric patients 14 days to 6 months of age should be taken into account in order to avoid toxicity from these excipients [see Warnings and Precautions (5.2) and Overdosage (10)].

Pediatric Dosage Calculations

Calculate the appropriate dose of KALETRA for each individual pediatric patient based on body weight (kg) or body surface area (BSA) to avoid underdosing or exceeding the recommended adult dose.

Body surface area (BSA) can be calculated as follows:

The KALETRA dose can be calculated based on weight or BSA:

Based on Weight:

Patient Weight (kg) × Prescribed lopinavir dose (mg/kg) = Administered lopinavir dose (mg)

Based on BSA:

Patient BSA (m^2) × Prescribed lopinavir dose (mg/m^2) = Administered lopinavir dose (mg)

If KALETRA oral solution is used, the volume (mL) of KALETRA solution can be determined as follows:

Volume of KALETRA solution (mL) = Administered lopinavir dose (mg) ÷ 80 (mg/mL)

Oral Solution Dosage Recommendation in Pediatric Patients 14 Days to Less Than 18 Years:

Table 4 summarizes the recommended daily dosing regimen for pediatric patients 14 days to less than 18 years of age using the oral solution.

KALETRA administered in combination with efavirenz, nevirapine, or nelfinavir in patients younger than 6 months of age is not recommended. Total dose of KALETRA oral solution in pediatric patients should not exceed the recommended adult daily dose of 400/100 mg (5mL) twice daily.

Table 4. KALETRA Oral Solution Daily Dosage Recommendations in Pediatric Patients 14 days to Less Than 18 Years Without Concomitant Efavirenz, Nevirapine, or Nelfinavir

Patient Age | Based on Weight (mg/kg) |  | Based on BSA (mg/m^2) | Frequency
14 days to 6 months | 16/4 |  | 300/75 | Given twice daily
Older than 6 months to less than 18 years | Less than15 kg | 12/3 | 230/57.5 | Given twice daily
 | 15 kg to 40 kg | 10/2.5

Tablet Dosage Recommendation in Pediatric Patients Older than 6 Months to Less than 18 Years:

Table 5 provides the dosing recommendations for pediatric patients older than 6 months to less than 18 years of age based on body weight or body surface area for KALETRA tablets.

Table 5. KALETRA Tablet Daily Dosage Recommendations in Pediatric Patients > 6 Months to < 18 Years of Age Without Concomitant Efavirenz, Nevirapine, or Nelfinavir

Body Weight (kg) | Body Surface Area (m^2)* | Recommended number of 100/25 mg Tablets Twice Daily
≥15 to 25 | ≥0.6 to < 0.9 | 2
>25 to 35 | ≥0.9 to < 1.4 | 3
>35 | ≥1.4 | 4
* KALETRA oral solution is available for children with a BSA less than 0.6 m^2 or those who are unable to reliably swallow a tablet.

Concomitant Therapy: Efavirenz, Nevirapine, or Nelfinavir

Dosing recommendations using oral solution

Table 6 provides the dosing recommendations for pediatric patients older than 6 months to less than 18 years of age based on body weight or body surface area for KALETRA Oral Solution when given in combination with efavirenz, nevirapine, or nelfinavir:

Table 6. KALETRA Oral Solution Daily Dosage Recommendations for Pediatric Patients > 6 Months to < 18 Years of Age With Concomitant Efavirenz, Nevirapine, or Nelfinavir

Patient Age | Based on Weight (mg/kg) |  | Based on BSA (mg/m^2) | Frequency
> 6 months to < 18 years | <15 kg | 13/3.25 | 300/75 | Given twice daily
 | ≥15 kg to 45 kg | 11/2.75

Dosing recommendations using tablets

Table 7 provides the dosing recommendations for pediatric patients older than 6 months to less than 18 years of age based on body weight or body surface area for KALETRA tablets when given in combination with efavirenz, nevirapine, or nelfinavir.

Table 7. KALETRA Tablet Daily Dosage Recommendations for Pediatric Patients > 6 Months to < 18 Years of Age With Concomitant Efavirenz†, Nevirapine, or Nelfinavir†

Body Weight (kg) | Body Surface Area (m^2)* | Recommended number of 100/25 mg Tablets Twice Daily
≥15 to 20 | ≥0.6 to < 0.8 | 2
>20 to 30 | ≥0.8 to < 1.2 | 3
>30 to 45 | ≥1.2 to <1.7 | 4
>45 | ≥1.7 | 5 [see Dosage and Administration (2.4)]
* KALETRA oral solution is available for children with a BSA less than 0.6 m^2 or those who are unable to reliably swallow a tablet.
† Please refer to the individual product labels for appropriate dosing in children.

2.5 Dosage Recommendations in Pregnancy

Administer 400/100 mg of KALETRA twice daily in pregnant patients with no documented lopinavir-associated resistance substitutions.

- Once daily KALETRA dosing is not recommended in pregnancy [see Use in Specific Populations (8.1) and Clinical Pharmacology (12.3)].
- There are insufficient data to recommend dosing in pregnant women with any documented lopinavir-associated resistance substitutions.
- No dosage adjustment of KALETRA is required for patients during the postpartum period.
- Avoid use of KALETRA oral solution in pregnant women [see Use in Specific Populations (8.1)].

3 DOSAGE FORMS AND STRENGTHS

- Tablets:
  ○ 200 mg lopinavir, 50 mg ritonavir: Yellow, film-coated, ovaloid, debossed with the “a” logo and the code KA containing 200 mg lopinavir and 50 mg ritonavir.
  ○ 100 mg lopinavir, 25 mg ritonavir: Pale yellow, film-coated, ovaloid, debossed with the “a” logo and the code KC containing 100 mg lopinavir and 25 mg ritonavir.
  ○ 200 mg lopinavir, 50 mg ritonavir: Red, film-coated, ovaloid, debossed with the code AL containing 200 mg lopinavir and 50 mg ritonavir.
  ○ 100 mg lopinavir, 25 mg ritonavir: Pink, film-coated, ovaloid, debossed with the code AC containing 100 mg lopinavir and 25 mg ritonavir.
- Oral Solution:
  ○ Light yellow to orange colored liquid containing 400 mg lopinavir and 100 mg ritonavir per 5 mL (80 mg lopinavir and 20 mg ritonavir per mL).

4 CONTRAINDICATIONS

- KALETRA is contraindicated in patients with previously demonstrated clinically significant hypersensitivity (e.g., toxic epidermal necrolysis, Stevens-Johnson syndrome, erythema multiforme, urticaria, angioedema) to any of its ingredients, including ritonavir.

- KALETRA is contraindicated with drugs that are highly dependent on CYP3A for clearance and for which elevated plasma concentrations are associated with serious and/or life-threatening reactions [see Drug Interactions (7.1) and Clinical Pharmacology (12.3)].
  ○ Alpha 1- Adrenoreceptor Antagonist: alfuzosin
  ○ Antianginal: ranolazine
  ○ Antiarrhythmic: dronedarone
  ○ Anti-gout: colchicine
  ○ Antipsychotics: lurasidone, pimozide
  ○ Ergot Derivatives: dihydroergotamine, ergotamine, methylergonovine
  ○ GI Motility Agent: cisapride
  ○ Hepatitis C direct acting antiviral: elbasvir/grazoprevir
  ○ HMG-CoA Reductase Inhibitors: lovastatin, simvastatin
  ○ Microsomal triglyceride transfer protein (MTTP) Inhibitor: lomitapide
  ○ PDE5 Inhibitor: sildenafil (Revatio®) when used for the treatment of pulmonary arterial hypertension
  ○ Sedative/Hypnotics: triazolam, orally administered midazolam
- KALETRA is contraindicated with drugs that are potent CYP3A inducers where significantly reduced lopinavir plasma concentrations may be associated with the potential for loss of virologic response and possible resistance and cross-resistance [see Drug Interactions (7.2) and Clinical Pharmacology (12.3)].
  ○ Anticancer Agents: apalutamide
  ○ Antimycobacterial: rifampin
  ○ Herbal Products: St. John's Wort (hypericum perforatum)

5 WARNINGS AND PRECAUTIONS

5.1 Risk of Serious Adverse Reactions Due to Drug Interactions

Initiation of KALETRA, a CYP3A inhibitor, in patients receiving medications metabolized by CYP3A or initiation of medications metabolized by CYP3A in patients already receiving KALETRA, may increase plasma concentrations of medications metabolized by CYP3A. Initiation of medications that inhibit or induce CYP3A may increase or decrease concentrations of KALETRA, respectively. These interactions may lead to:

- Clinically significant adverse reactions, potentially leading to severe, life-threatening, or fatal events from greater exposures of concomitant medications.
- Clinically significant adverse reactions from greater exposures of KALETRA.
- Loss of therapeutic effect of KALETRA and possible development of resistance.

See Table 12 for steps to prevent or manage these possible and known significant drug interactions, including dosing recommendations [see Drug Interactions (7)]. Consider the potential for drug interactions prior to and during KALETRA therapy; review concomitant medications during KALETRA therapy, and monitor for the adverse reactions associated with the concomitant medications [see Contraindications (4) and Drug Interactions (7)].

5.2 Toxicity in Preterm Neonates

KALETRA oral solution contains the excipients ethanol, approximately 42% (v/v) and propylene glycol, approximately 15% (w/v). When administered concomitantly with propylene glycol, ethanol competitively inhibits the metabolism of propylene glycol, which may lead to elevated concentrations. Preterm neonates may be at increased risk of propylene glycol-associated adverse events due to diminished ability to metabolize propylene glycol, thereby leading to accumulation and potential adverse events. Postmarketing life-threatening cases of cardiac toxicity (including complete AV block, bradycardia, and cardiomyopathy), lactic acidosis, acute renal failure, CNS depression and respiratory complications leading to death have been reported, predominantly in preterm neonates receiving KALETRA oral solution.

KALETRA oral solution should not be used in preterm neonates in the immediate postnatal period because of possible toxicities. A safe and effective dose of KALETRA oral solution in this patient population has not been established. However, if the benefit of using KALETRA oral solution to treat HIV infection in infants immediately after birth outweighs the potential risks, infants should be monitored closely for increases in serum osmolality and serum creatinine, and for toxicity related to KALETRA oral solution including: hyperosmolality, with or without lactic acidosis, renal toxicity, CNS depression (including stupor, coma, and apnea), seizures, hypotonia, cardiac arrhythmias and ECG changes, and hemolysis. Total amounts of ethanol and propylene glycol from all medicines that are to be given to infants should be taken into account in order to avoid toxicity from these excipients [see Dosage and Administration (2.4) and Overdosage (10)].

5.3 Pancreatitis

Pancreatitis has been observed in patients receiving KALETRA therapy, including those who developed marked triglyceride elevations. In some cases, fatalities have been observed. Although a causal relationship to KALETRA has not been established, marked triglyceride elevations are a risk factor for development of pancreatitis [see Warnings and Precautions (5.9)]. Patients with advanced HIV-1 disease may be at increased risk of elevated triglycerides and pancreatitis, and patients with a history of pancreatitis may be at increased risk for recurrence during KALETRA therapy.

Pancreatitis should be considered if clinical symptoms (nausea, vomiting, abdominal pain) or abnormalities in laboratory values (such as increased serum lipase or amylase values) suggestive of pancreatitis occur. Patients who exhibit these signs or symptoms should be evaluated and KALETRA and/or other antiretroviral therapy should be suspended as clinically appropriate.

5.4 Hepatotoxicity

Patients with underlying hepatitis B or C or marked elevations in transaminase prior to treatment may be at increased risk for developing or worsening of transaminase elevations or hepatic decompensation with use of KALETRA.

There have been postmarketing reports of hepatic dysfunction, including some fatalities. These have generally occurred in patients with advanced HIV-1 disease taking multiple concomitant medications in the setting of underlying chronic hepatitis or cirrhosis. A causal relationship with KALETRA therapy has not been established.

Elevated transaminases with or without elevated bilirubin levels have been reported in HIV-1 mono-infected and uninfected patients as early as 7 days after the initiation of KALETRA in conjunction with other antiretroviral agents. In some cases, the hepatic dysfunction was serious; however, a definitive causal relationship with KALETRA therapy has not been established.

Appropriate laboratory testing should be conducted prior to initiating therapy with KALETRA and patients should be monitored closely during treatment. Increased AST/ALT monitoring should be considered in the patients with underlying chronic hepatitis or cirrhosis, especially during the first several months of KALETRA treatment [see Use in Specific Populations (8.6)].

5.5 QT Interval Prolongation

Postmarketing cases of QT interval prolongation and torsade de pointes have been reported although causality of KALETRA could not be established. Avoid use in patients with congenital long QT syndrome, those with hypokalemia, and with other drugs that prolong the QT interval [see Clinical Pharmacology (12.3)].

5.6 PR Interval Prolongation

Lopinavir/ritonavir prolongs the PR interval in some patients. Cases of second or third degree atrioventricular block have been reported. KALETRA should be used with caution in patients with underlying structural heart disease, pre-existing conduction system abnormalities, ischemic heart disease or cardiomyopathies, as these patients may be at increased risk for developing cardiac conduction abnormalities.

The impact on the PR interval of co-administration of KALETRA with other drugs that prolong the PR interval (including calcium channel blockers, beta-adrenergic blockers, digoxin and atazanavir) has not been evaluated. As a result, co-administration of KALETRA with these drugs should be undertaken with caution, particularly with those drugs metabolized by CYP3A. Clinical monitoring is recommended [see Clinical Pharmacology (12.3)].

5.7 Diabetes Mellitus/Hyperglycemia

New onset diabetes mellitus, exacerbation of pre-existing diabetes mellitus, and hyperglycemia have been reported during post-marketing surveillance in HIV-1 infected patients receiving protease inhibitor therapy. Some patients required either initiation or dose adjustments of insulin or oral hypoglycemic agents for treatment of these events. In some cases, diabetic ketoacidosis has occurred. In those patients who discontinued protease inhibitor therapy, hyperglycemia persisted in some cases. Because these events have been reported voluntarily during clinical practice, estimates of frequency cannot be made and a causal relationship between protease inhibitor therapy and these events has not been established. Consider monitoring for hyperglycemia, new onset diabetes mellitus or an exacerbation of diabetes mellitus in patients treated with KALETRA.

5.8 Immune Reconstitution Syndrome

Immune reconstitution syndrome has been reported in patients treated with combination antiretroviral therapy, including KALETRA. During the initial phase of combination antiretroviral treatment, patients whose immune system responds may develop an inflammatory response to indolent or residual opportunistic infections (such as Mycobacterium avium infection, cytomegalovirus, Pneumocystis jirovecii pneumonia [PCP], or tuberculosis) which may necessitate further evaluation and treatment.

Autoimmune disorders (such as Graves’ disease, polymyositis, and Guillain-Barré syndrome) have also been reported to occur in the setting of immune reconstitution, however, the time to onset is more variable, and can occur many months after initiation of treatment.

5.9 Lipid Elevations

Treatment with KALETRA has resulted in large increases in the concentration of total cholesterol and triglycerides [see Adverse Reactions (6.1)]. Triglyceride and cholesterol testing should be performed prior to initiating KALETRA therapy and at periodic intervals during therapy. Lipid disorders should be managed as clinically appropriate, taking into account any potential drug-drug interactions with KALETRA and HMG-CoA reductase inhibitors [see Contraindications (4) and Drug Interactions (7.3)].

5.10 Fat Redistribution

Redistribution/accumulation of body fat including central obesity, dorsocervical fat enlargement (buffalo hump), peripheral wasting, facial wasting, breast enlargement, and "cushingoid appearance" have been observed in patients receiving antiretroviral therapy. The mechanism and long-term consequences of these events are currently unknown. A causal relationship has not been established.

5.11 Patients with Hemophilia

Increased bleeding, including spontaneous skin hematomas and hemarthrosis have been reported in patients with hemophilia type A and B treated with protease inhibitors. In some patients additional factor VIII was given. In more than half of the reported cases, treatment with protease inhibitors was continued or reintroduced. A causal relationship between protease inhibitor therapy and these events has not been established.

5.12 Resistance/Cross-resistance

Because the potential for HIV cross-resistance among protease inhibitors has not been fully explored in KALETRA-treated patients, it is unknown what effect therapy with KALETRA will have on the activity of subsequently administered protease inhibitors [see Microbiology (12.4)].

6 ADVERSE REACTIONS

The following adverse reactions are discussed in greater detail in other sections of the labeling.

- QT Interval Prolongation, PR Interval Prolongation [see Warnings and Precautions (5.5, 5.6)]
- Drug Interactions [see Warnings and Precautions (5.1)]
- Pancreatitis [see Warnings and Precautions (5.3)]
- Hepatotoxicity [see Warnings and Precautions (5.4)]

6.1 Clinical Trials Experience

Because clinical trials are conducted under widely varying conditions, adverse reactions rates observed in the clinical trials of a drug cannot be directly compared to rates in the clinical trials of another drug and may not reflect the rates observed in clinical practice.

Adverse Reactions in Adults

The safety of KALETRA has been investigated in about 2,600 patients in Phase II-IV clinical trials, of which about 700 have received a dose of 800/200 mg (6 capsules or 4 tablets) once daily. Along with nucleoside reverse transcriptase inhibitors (NRTIs), in some studies, KALETRA was used in combination with efavirenz or nevirapine.

In clinical studies the incidence of diarrhea in patients treated with either KALETRA capsules or tablets was greater in those patients treated once daily than in those patients treated twice daily. Any grade of diarrhea was reported by at least half of patients taking once daily Kaletra capsules or tablets. At the time of treatment discontinuation, 4.2-6.3% of patients taking once daily Kaletra and 1.8-3.7% of those taking twice daily Kaletra reported ongoing diarrhea.

Commonly reported adverse reactions to KALETRA included diarrhea, nausea, vomiting, hypertriglyceridemia and hypercholesterolemia. Diarrhea, nausea and vomiting may occur at the beginning of the treatment while hypertriglyceridemia and hypercholesterolemia may occur later. The following have been identified as adverse reactions of moderate or severe intensity (Table 8):

Table 8. Adverse Reactions of Moderate or Severe Intensity Occurring in at Least 0.1% of Adult Patients Receiving KALETRA in Combined Phase II/IV Studies (N=2,612)

System Organ Class (SOC) and Adverse Reaction | n | %
BLOOD AND LYMPHATIC SYSTEM DISORDERS
anemia* | 54 | 2.1
leukopenia and neutropenia* | 44 | 1.7
lymphadenopathy* | 35 | 1.3
CARDIAC DISORDERS
atherosclerosis such as myocardial infarction* | 10 | 0.4
atrioventricular block* | 3 | 0.1
tricuspid valve incompetence* | 3 | 0.1
EAR AND LABYRINTH DISORDERS
vertigo* | 7 | 0.3
tinnitus | 6 | 0.2
ENDOCRINE DISORDERS
hypogonadism* | 16 | 0.8^1
EYE DISORDERS
visual impairment* | 8 | 0.3
GASTROINTESTINAL DISORDERS
diarrhea* | 510 | 19.5
nausea | 269 | 10.3
vomiting* | 177 | 6.8
abdominal pain (upper and lower)* | 160 | 6.1
gastroenteritis and colitis* | 66 | 2.5
dyspepsia | 53 | 2.0
pancreatitis* | 45 | 1.7
Gastroesophageal Reflux Disease (GERD)* | 40 | 1.5
hemorrhoids | 39 | 1.5
flatulence | 36 | 1.4
abdominal distension | 34 | 1.3
constipation* | 26 | 1.0
stomatitis and oral ulcers* | 24 | 0.9
duodenitis and gastritis* | 20 | 0.8
gastrointestinal hemorrhage including rectal hemorrhage* | 13 | 0.5
dry mouth | 9 | 0.3
gastrointestinal ulcer* | 6 | 0.2
fecal incontinence | 5 | 0.2
GENERAL DISORDERS AND ADMINISTRATION SITE CONDITIONS
fatigue including asthenia* | 198 | 7.6
HEPATOBILIARY DISORDERS
hepatitis including AST, ALT, and GGT increases* | 91 | 3.5
hepatomegaly | 5 | 0.2
cholangitis | 3 | 0.1
hepatic steatosis | 3 | 0.1
IMMUNE SYSTEM DISORDERS
hypersensitivity including urticaria and angioedema* | 70 | 2.7
immune reconstitution syndrome | 3 | 0.1
INFECTIONS AND INFESTATIONS
upper respiratory tract infection* | 363 | 13.9
lower respiratory tract infection* | 202 | 7.7
skin infections including cellulitis, folliculitis, and furuncle* | 86 | 3.3
METABOLISM AND NUTRITION DISORDERS
hypercholesterolemia* | 192 | 7.4
hypertriglyceridemia* | 161 | 6.2
weight decreased* | 61 | 2.3
decreased appetite | 52 | 2.0
blood glucose disorders including diabetes mellitus* | 30 | 1.1
weight increased* | 20 | 0.8
lactic acidosis* | 11 | 0.4
increased appetite | 5 | 0.2
MUSCULOSKELETAL AND CONNECTIVE TISSUE DISORDERS
musculoskeletal pain including arthralgia and back pain* | 166 | 6.4
myalgia* | 46 | 1.8
muscle disorders such as weakness and spasms* | 34 | 1.3
rhabdomyolysis* | 18 | 0.7
osteonecrosis | 3 | 0.1
NERVOUS SYSTEM DISORDERS
headache including migraine* | 165 | 6.3
insomnia* | 99 | 3.8
neuropathy and peripheral neuropathy* | 51 | 2.0
dizziness* | 45 | 1.7
ageusia* | 19 | 0.7
convulsion* | 9 | 0.3
tremor* | 9 | 0.3
cerebral vascular event* | 6 | 0.2
PSYCHIATRIC DISORDERS
anxiety* | 101 | 3.9
abnormal dreams* | 19 | 0.7
libido decreased | 19 | 0.7
RENAL AND URINARY DISORDERS
renal failure* | 31 | 1.2
hematuria* | 20 | 0.8
nephritis* | 3 | 0.1
REPRODUCTIVE SYSTEM AND BREAST DISORDERS
erectile dysfunction* | 34 | 1.7^1
menstrual disorders - amenorrhea, menorrhagia* | 10 | 1.7^2
SKIN AND SUBCUTANEOUS TISSUE DISORDERS
rash including maculopapular rash* | 99 | 3.8
lipodystrophy acquired including facial wasting* | 58 | 2.2
dermatitis/rash including eczema and seborrheic dermatitis* | 50 | 1.9
night sweats* | 42 | 1.6
pruritus* | 29 | 1.1
alopecia | 10 | 0.4
capillaritis and vasculitis* | 3 | 0.1
VASCULAR DISORDERS
hypertension* | 47 | 1.8
deep vein thrombosis* | 17 | 0.7
*Represents a medical concept including several similar MedDRA PTs
^1. Percentage of male population (N=2,038)
^2. Percentage of female population (N=574)

Laboratory Abnormalities in Adults

The percentages of adult patients treated with combination therapy with Grade 3-4 laboratory abnormalities are presented in Table 9 (treatment-naïve patients) and Table 10 (treatment-experienced patients).

Table 9. Grade 3-4 Laboratory Abnormalities Reported in ≥ 2% of Adult Antiretroviral-Naïve Patients

 |  | Study 863 (48 Weeks) |  | Study 720 (360 Weeks) | Study 730 (48 Weeks)
Variable | Limit^1 | KALETRA 400/100 mg Twice Daily + d4T +3TC (N = 326) | Nelfinavir 750 mg Three Times Daily + d4T + 3TC (N = 327) | KALETRA Twice Daily + d4T + 3TC (N = 100) | KALETRA Once Daily + TDF +FTC (N=333) | KALETRA Twice Daily + TDF +FTC (N=331)
Chemistry | High
Glucose | > 250 mg/dL | 2% | 2% | 4% | 0% | <1%
Uric Acid | > 12 mg/dL | 2% | 2% | 5% | <1% | 1%
SGOT/ AST^2 | > 180 U/L | 2% | 4% | 10% | 1% | 2%
SGPT/ ALT^2 | >215 U/L | 4% | 4% | 11% | 1% | 1%
GGT | >300 U/L | N/A | N/A | 10% | N/A | N/A
Total Cholesterol | >300 mg/dL | 9% | 5% | 27% | 4% | 3%
Triglycerides | >750 mg/dL | 9% | 1% | 29% | 3% | 6%
Amylase | >2 x ULN | 3% | 2% | 4% | N/A | N/A
Lipase | >2 x ULN | N/A | N/A | N/A | 3% | 5%
Chemistry | Low
Calculated Creatinine Clearance | <50 mL/min | N/A | N/A | N/A | 2% | 2%
Hematology | Low
Neutrophils | <0.75 x 10^9/L | 1% | 3% | 5% | 2% | 1%
1 ULN = upper limit of the normal range; N/A = Not Applicable.
2 Criterion for Study 730 was >5x ULN (AST/ALT).

Table 10. Grade 3-4 Laboratory Abnormalities Reported in ≥ 2% of Adult Protease Inhibitor-Experienced Patients

 |  | Study 888 (48 Weeks) |  | Study 957^2 and Study 765^3 (84-144 Weeks) | Study 802 (48 Weeks)
Variable | Limit^1 | KALETRA 400/100 mg Twice Daily + NVP + NRTIs (N = 148) | Investigator-Selected Protease Inhibitor(s) + NVP + NRTIs (N = 140) | KALETRA Twice Daily + NNRTI + NRTIs (N = 127) | KALETRA 800/200 mg Once Daily +NRTIs (N=300) | KALETRA 400/100 mg Twice Daily +NRTIs (N=299)
Chemistry | High
Glucose | >250 mg/dL | 1% | 2% | 5% | 2% | 2%
Total Bilirubin | >3.48 mg/dL | 1% | 3% | 1% | 1% | 1%
SGOT/AST^4 | >180 U/L | 5% | 11% | 8% | 3% | 2%
SGPT/ALT^4 | >215 U/L | 6% | 13% | 10% | 2% | 2%
GGT | >300 U/L | N/A | N/A | 29% | N/A | N/A
Total Cholesterol | >300 mg/dL | 20% | 21% | 39% | 6% | 7%
Triglycerides | >750 mg/dL | 25% | 21% | 36% | 5% | 6%
Amylase | >2 x ULN | 4% | 8% | 8% | 4% | 4%
Lipase | >2 x ULN | N/A | N/A | N/A | 4% | 1%
Creatine Phosphokinase | >4 x ULN | N/A | N/A | N/A | 4% | 5%
Chemistry | Low
Calculated Creatinine Clearance | <50 mL/min | N/A | N/A | N/A | 3% | 3%
Inorganic Phosphorus | <1.5 mg/dL | 1% | 0% | 2% | 1% | <1%
Hematology | Low
Neutrophils | <0.75 x 10^9/L | 1% | 2% | 4% | 3% | 4%
Hemoglobin | <80 g/L | 1% | 1% | 1% | 1% | 2%
1 ULN = upper limit of the normal range; N/A = Not Applicable.
2 Includes clinical laboratory data from patients receiving 400/100 mg twice daily (n = 29) or 533/133 mg twice daily (n = 28) for 84 weeks. Patients received KALETRA in combination with NRTIs and efavirenz.
3 Includes clinical laboratory data from patients receiving 400/100 mg twice daily (n = 36) or 400/200 mg twice daily (n = 34) for 144 weeks. Patients received KALETRA in combination with NRTIs and nevirapine.
4 Criterion for Study 802 was >5x ULN (AST/ALT).

Adverse Reactions in Pediatric Patients

KALETRA oral solution dosed up to 300/75 mg/m^2 has been studied in 100 pediatric patients 6 months to 12 years of age. The adverse reaction profile seen during Study 940 was similar to that for adult patients.

Dysgeusia (22%), vomiting (21%), and diarrhea (12%) were the most common adverse reactions of any severity reported in pediatric patients treated with combination therapy for up to 48 weeks in Study 940. A total of 8 patients experienced adverse reactions of moderate to severe intensity. The adverse reactions meeting these criteria and reported for the 8 subjects include: hypersensitivity (characterized by fever, rash and jaundice), pyrexia, viral infection, constipation, hepatomegaly, pancreatitis, vomiting, alanine aminotransferase increased, dry skin, rash, and dysgeusia. Rash was the only event of those listed that occurred in 2 or more subjects (N = 3).

KALETRA oral solution dosed at 300/75 mg/m^2 has been studied in 31 pediatric patients 14 days to 6 months of age. The adverse reaction profile in Study 1030 was similar to that observed in older children and adults. No adverse reaction was reported in greater than 10% of subjects. Adverse drug reactions of moderate to severe intensity occurring in 2 or more subjects included decreased neutrophil count (N=3), anemia (N=2), high potassium (N=2), and low sodium (N=2).

KALETRA oral solution and soft gelatin capsules dosed at higher than recommended doses including 400/100 mg/m^2 (without concomitant NNRTI) and 480/120 mg/m^2 (with concomitant NNRTI) have been studied in 26 pediatric patients 7 to 18 years of age in Study 1038. Patients also had saquinavir mesylate added to their regimen at Week 4. Rash (12%), blood cholesterol abnormal (12%) and blood triglycerides abnormal (12%) were the only adverse reactions reported in greater than 10% of subjects. Adverse drug reactions of moderate to severe intensity occurring in 2 or more subjects included rash (N=3), blood triglycerides abnormal (N=3), and electrocardiogram QT prolonged (N=2). Both subjects with QT prolongation had additional predisposing conditions such as electrolyte abnormalities, concomitant medications, or pre-existing cardiac abnormalities.

Laboratory Abnormalities in Pediatric Patients

The percentages of pediatric patients treated with combination therapy including KALETRA with Grade 3-4 laboratory abnormalities are presented in Table 11.

Table 11. Grade 3-4 Laboratory Abnormalities Reported in ≥ 2% Pediatric Patients in Study 940

Variable | Limit^1 | KALETRA Twice Daily + RTIs (N = 100)
Chemistry | High
Sodium | > 149 mEq/L | 3%
Total Bilirubin | ≥ 3.0 x ULN | 3%
SGOT/AST | > 180 U/L | 8%
SGPT/ALT | > 215 U/L | 7%
Total Cholesterol | > 300 mg/dL | 3%
Amylase | > 2.5 x ULN | 7%^2
Chemistry | Low
Sodium | < 130 mEq/L | 3%
Hematology | Low
Platelet Count | < 50 x 10^9/L | 4%
Neutrophils | < 0.40 x 10^9/L | 2%
1 ULN = upper limit of the normal range.
2 Subjects with Grade 3-4 amylase confirmed by elevations in pancreatic amylase.

6.2 Postmarketing Experience

The following adverse reactions have been reported during postmarketing use of KALETRA. Because these reactions are reported voluntarily from a population of unknown size, it is not possible to reliably estimate their frequency or establish a causal relationship to KALETRA exposure.

Body as a Whole
Redistribution/accumulation of body fat has been reported [see Warnings and Precautions (5.10)].

Cardiovascular
Bradyarrhythmias. First-degree AV block, second-degree AV block, third-degree AV block, QTc interval prolongation, torsades (torsade) de pointes [see Warnings and Precautions (5.5, 5.6)].

Renal and Urinary Disorders
Nephrolithiasis

Skin and Appendages
Toxic epidermal necrolysis (TEN), Stevens-Johnson syndrome and erythema multiforme.

7 DRUG INTERACTIONS

7.1 Potential for KALETRA to Affect Other Drugs

Lopinavir/ritonavir is an inhibitor of CYP3A and may increase plasma concentrations of agents that are primarily metabolized by CYP3A. Agents that are extensively metabolized by CYP3A and have high first pass metabolism appear to be the most susceptible to large increases in AUC (> 3-fold) when co-administered with KALETRA. Thus, co-administration of KALETRA with drugs highly dependent on CYP3A for clearance and for which elevated plasma concentrations are associated with serious and/or life-threatening events is contraindicated. Co-administration with other CYP3A substrates may require a dose adjustment or additional monitoring as shown in Table 12.

Additionally, KALETRA induces glucuronidation.

Published data suggest that lopinavir is an inhibitor of OATP1B1.

These examples are a guide and not considered a comprehensive list of all possible drugs that may interact with lopinavir/ritonavir. The healthcare provider should consult appropriate references for comprehensive information.

7.2 Potential for Other Drugs to Affect Lopinavir

Lopinavir/ritonavir is a CYP3A substrate; therefore, drugs that induce CYP3A may decrease lopinavir plasma concentrations and reduce KALETRA’s therapeutic effect. Although not observed in the KALETRA/ketoconazole drug interaction study, co-administration of KALETRA and other drugs that inhibit CYP3A may increase lopinavir plasma concentrations.

7.3 Established and Other Potentially Significant Drug Interactions

Table 12 provides a listing of established or potentially clinically significant drug interactions. Alteration in dose or regimen may be recommended based on drug interaction studies or predicted interaction [see Contraindications (4), Warnings and Precautions (5.1), Clinical Pharmacology (12.3)] for magnitude of interaction.

Table 12. Established and Other Potentially Significant Drug Interactions

Concomitant Drug Class: Drug Name | Effect on Concentration of Lopinavir or Concomitant Drug | Clinical Comments
HIV-1 Antiviral Agents
HIV-1 Protease Inhibitor: fosamprenavir/ritonavir | ↓ amprenavir ↓ lopinavir | An increased rate of adverse reactions has been observed with co-administration of these medications. Appropriate doses of the combinations with respect to safety and efficacy have not been established.
HIV-1 Protease Inhibitor: indinavir* | ↑ indinavir | Decrease indinavir dose to 600 mg twice daily, when co-administered with KALETRA 400/100 mg twice daily. KALETRA once daily has not been studied in combination with indinavir.
HIV-1 Protease Inhibitor: nelfinavir* | ↑ nelfinavir ↑ M8 metabolite of nelfinavir ↓ lopinavir | KALETRA once daily in combination with nelfinavir is not recommended [see Dosage and Administration (2)].
HIV-1 Protease Inhibitor: ritonavir* | ↑ lopinavir | Appropriate doses of additional ritonavir in combination with KALETRA with respect to safety and efficacy have not been established.
HIV-1 Protease Inhibitor: saquinavir | ↑ saquinavir | The saquinavir dose is 1000 mg twice daily, when co-administered with KALETRA 400/100 mg twice daily. KALETRA once daily has not been studied in combination with saquinavir.
HIV-1 Protease Inhibitor: tipranavir* | ↓ lopinavir | Co-administration with tipranavir (500 mg twice daily) and ritonavir (200 mg twice daily) is not recommended.
HIV CCR5 – Antagonist: maraviroc* | ↑ maraviroc | When co-administered, patients should receive 150 mg twice daily of maraviroc. For further details see complete prescribing information for maraviroc.
Non-nucleoside Reverse Transcriptase Inhibitors: efavirenz*, nevirapine* | ↓ lopinavir | Increase the dose of KALETRA tablets to 500/125 mg when KALETRA tablet is co-administered with efavirenz or nevirapine. KALETRA once daily in combination with efavirenz or nevirapine is not recommended [see Dosage and Administration (2)].
Non-nucleoside Reverse Transcriptase Inhibitor: delavirdine | ↑ lopinavir | Appropriate doses of the combination with respect to safety and efficacy have not been established.
Nucleoside Reverse Transcriptase Inhibitor: didanosine |  | KALETRA tablets can be administered simultaneously with didanosine without food. For KALETRA oral solution, it is recommended that didanosine be administered on an empty stomach; therefore, didanosine should be given one hour before or two hours after KALETRA oral solution (given with food).
Nucleoside Reverse Transcriptase Inhibitor: tenofovir disoproxil fumarate* | ↑ tenofovir | Patients receiving KALETRA and tenofovir should be monitored for adverse reactions associated with tenofovir.
Nucleoside Reverse Transcriptase Inhibitors: abacavir zidovudine | ↓ abacavir ↓ zidovudine | The clinical significance of this potential interaction is unknown.
Other Agents
Alpha 1- Adrenoreceptor Antagonist: alfuzosin | ↑ alfuzosin | Contraindicated due to potential hypotension [see Contraindications (4)].
Antianginal: ranolazine | ↑ ranolazine | Contraindicated due to potential for serious and/or life-threatening reactions [see Contraindications (4)].
Antiarrhythmics: dronedarone | ↑ dronedarone | Contraindicated due to potential for cardiac arrhythmias [see Contraindications (4)].
Antiarrhythmics e.g. amiodarone, bepridil, lidocaine (systemic), quinidine | ↑ antiarrhythmics | Caution is warranted and therapeutic concentration monitoring (if available) is recommended for antiarrhythmics when co-administered with KALETRA.
Anticancer Agents: abemaciclib, apalutamide, encorafenib, ibrutinib, ivosidenib, dasatinib, neratinib, nilotinib, venetoclax, vinblastine, vincristine | ↑ anticancer agents ↓lopinavir/ritonavir# | Apalutamide is contraindicated due to potential for loss of virologic response and possible resistance to KALETRA or to the class of protease inhibitors [see Contraindications (4)]. Avoid co-administration of encorafenib or ivosidenib with KALETRA due to potential risk of serious adverse events such as QT interval prolongation. If co-administration of encorafenib with KALETRA cannot be avoided, modify dose as recommended in encorafenib USPI. If co-administration of ivosidenib with KALETRA cannot be avoided, reduce ivosidenib dose to 250 mg once daily. Avoid use of neratinib, venetoclax or ibrutinib with KALETRA. For vincristine and vinblastine, consideration should be given to temporarily withholding the ritonavir-containing antiretroviral regimen in patients who develop significant hematologic or gastrointestinal side effects when KALETRA is administered concurrently with vincristine or vinblastine. If the antiretroviral regimen must be withheld for a prolonged period, consideration should be given to initiating a revised regimen that does not include a CYP3A or P-gp inhibitor. A decrease in the dosage or an adjustment of the dosing interval of nilotinib and dasatinib may be necessary for patients requiring co-administration with strong CYP3A inhibitors such as KALETRA. Please refer to the nilotinib and dasatinib prescribing information for dosing instructions.
Anticoagulants: warfarin, rivaroxaban | ↑↓ warfarin ↑ rivaroxaban | Concentrations of warfarin may be affected. Initial frequent monitoring of the INR during KALETRA and warfarin co-administration is recommended. Avoid concomitant use of rivaroxaban and KALETRA. Co-administration of KALETRA and rivaroxaban may lead to increased risk of bleeding.
Anticonvulsants: carbamazepine, phenobarbital, phenytoin | ↓ lopinavir ↓ phenytoin | KALETRA may be less effective due to decreased lopinavir plasma concentrations in patients taking these agents concomitantly and should be used with caution. KALETRA once daily in combination with carbamazepine, phenobarbital, or phenytoin is not recommended. In addition, co-administration of phenytoin and KALETRA may cause decreases in steady-state phenytoin concentrations. Phenytoin levels should be monitored when co-administering with KALETRA.
Anticonvulsants: lamotrigine, valproate | ↓ lamotrigine ↓ or ↔ valproate | A dose increase of lamotrigine or valproate may be needed when co-administered with KALETRA and therapeutic concentration monitoring for lamotrigine may be indicated; particularly during dosage adjustments.
Antidepressant: bupropion | ↓ bupropion ↓ active metabolite, hydroxybupropion | Patients receiving KALETRA and bupropion concurrently should be monitored for an adequate clinical response to bupropion.
Antidepressant: trazodone | ↑ trazodone | Adverse reactions of nausea, dizziness, hypotension and syncope have been observed following co-administration of trazodone and ritonavir. A lower dose of trazodone should be considered.
Anti-infective: clarithromycin | ↑ clarithromycin | For patients with renal impairment, adjust clarithromycin dose as follows:; - For patients on KALETRA with CLCR 30 to 60 mL/min the dose of clarithromycin should be reduced by 50%. - For patients on KALETRA with CLCR < 30 mL/min the dose of clarithromycin should be decreased by 75%.; No dose adjustment for patients with normal renal function is necessary.
Antifungals: ketoconazole*, itraconazole, voriconazole isavuconazonium sulfate* | ↑ ketoconazole ↑ itraconazole ↓ voriconazole ↑ isavuconazonium | High doses of ketoconazole (>200 mg/day) or itraconazole (> 200 mg/day) are not recommended. The coadministration of voriconazole and KALETRA should be avoided unless an assessment of the benefit/risk to the patient justifies the use of voriconazole. Isavuconazonium and Kaletra should be coadministered with caution. Alternative antifungal therapies should be considered in these patients.
Anti-gout: colchicine | ↑ colchicine | Contraindicated due to potential for serious and/or life-threatening reactions in patients with renal and/or hepatic impairment [see Contraindications (4)]. For patients with normal renal or hepatic function: Treatment of gout flares-co-administration of colchicine in patients on KALETRA: 0.6 mg (1 tablet) x 1 dose, followed by 0.3 mg (half tablet) 1 hour later. Dose to be repeated no earlier than 3 days. Prophylaxis of gout flares-co-administration of colchicine in patients on KALETRA: If the original colchicine regimen was 0.6 mg twice a day, the regimen should be adjusted to 0.3 mg once a day. If the original colchicine regimen was 0.6 mg once a day, the regimen should be adjusted to 0.3 mg once every other day. Treatment of familial Mediterranean fever (FMF)-co-administration of colchicine in patients on KALETRA: Maximum daily dose of 0.6 mg (may be given as 0.3 mg twice a day).
Antimycobacterial: rifampin | ↓ lopinavir | Contraindicated due to potential loss of virologic response and possible resistance to KALETRA or to the class of protease inhibitors or other co-administered antiretroviral agents [see Contraindications (4)].
Antimycobacterial: bedaquiline | ↑ bedaquiline | Bedaquiline should only be used with KALETRA if the benefit of co-administration outweighs the risk.
Antimycobacterial: rifabutin* | ↑ rifabutin and rifabutin metabolite | Dosage reduction of rifabutin by at least 75% of the usual dose of 300 mg/day is recommended (i.e., a maximum dose of 150 mg every other day or three times per week). Increased monitoring for adverse reactions is warranted in patients receiving the combination. Further dosage reduction of rifabutin may be necessary.
Antiparasitic: atovaquone | ↓ atovaquone | Clinical significance is unknown; however, increase in atovaquone doses may be needed.
Antipsychotics: lurasidone pimozide | ↑ lurasidone ↑ pimozide | Contraindicated due to potential for serious and/or life-threatening reactions [see Contraindications (4)]. Contraindicated due to potential for serious and/or life-threatening reactions such as cardiac arrhythmias [see Contraindications (4)].
Antipsychotics: quetiapine | ↑ quetiapine | Initiation of KALETRA in patients taking quetiapine: Consider alternative antiretroviral therapy to avoid increases in quetiapine exposures. If coadministration is necessary, reduce the quetiapine dose to 1/6 of the current dose and monitor for quetiapine-associated adverse reactions. Refer to the quetiapine prescribing information for recommendations on adverse reaction monitoring. Initiation of quetiapine in patients taking KALETRA: Refer to the quetiapine prescribing information for initial dosing and titration of quetiapine.
Contraceptive: ethinyl estradiol* | ↓ ethinyl estradiol | Because contraceptive steroid concentrations may be altered when KALETRA is co-administered with oral contraceptives or with the contraceptive patch, alternative methods of nonhormonal contraception are recommended.
Dihydropyridine Calcium Channel Blockers: e.g. felodipine, nifedipine, nicardipine | ↑ dihydropyridine calcium channel blockers | Clinical monitoring of patients is recommended and a dose reduction of the dihydropyridine calcium channel blocker may be considered.
Disulfiram/metronidazole |  | KALETRA oral solution contains ethanol, which can produce disulfiram-like reactions when co-administered with disulfiram or other drugs that produce this reaction (e.g., metronidazole).
Endothelin Receptor Antagonists: bosentan | ↑ bosentan | Co-administration of bosentan in patients on KALETRA: In patients who have been receiving KALETRA for at least 10 days, start bosentan at 62.5 mg once daily or every other day based upon individual tolerability. Co-administration of KALETRA in patients on bosentan: Discontinue use of bosentan at least 36 hours prior to initiation of KALETRA. After at least 10 days following the initiation of KALETRA, resume bosentan at 62.5 mg once daily or every other day based upon individual tolerability.
Ergot Derivatives: dihydroergotamine, ergotamine, methylergonovine | ↑ ergot derivatives | Contraindicated due to potential for acute ergot toxicity characterized by peripheral vasospasm and ischemia of the extremities and other tissues [see Contraindications (4)].
GI Motility Agent: cisapride | ↑ cisapride | Contraindicated due to potential for cardiac arrhythmias [see Contraindications (4)].
GnRH Receptor Antagonists: elagolix | ↑ elagolix ↓ lopinavir/ritonavir | Concomitant use of elagolix 200 mg twice daily and KALETRA for more than 1 month is not recommended due to potential risk of adverse events such as bone loss and hepatic transaminase elevations. Limit concomitant use of elagolix 150 mg once daily and KALETRA to 6 months.
Hepatitis C direct acting antiviral: elbasvir/grazoprevir | ↑ elbasvir/grazoprevir | Contraindicated due to increased risk of alanine transaminase (ALT) elevations [see Contraindications (4)].
Hepatitis C direct acting antivirals: boceprevir* glecaprevir/pibrentasvir simeprevir sofosbuvir/velpatasvir/voxilaprevir ombitasvir/paritaprevir/ ritonavir and dasabuvir* | ↓ lopinavir ↓ boceprevir ↓ ritonavir ↑glecaprevir ↑ pibrentasvir ↑ simeprevir ↑ sofosbuvir ↑ velpatasvir ↑ voxilaprevir ↑ ombitasvir ↑ paritaprevir ↑ ritonavir ↔ dasabuvir | It is not recommended to co-administer KALETRA and boceprevir, glecaprevir/pibrentasvir, simeprevir, sofosbuvir/velpatasvir/voxilaprevir, or ombitasvir/paritaprevir/ritonavir and dasabuvir.
Herbal Products: St. John's Wort (hypericum perforatum) | ↓ lopinavir | Contraindicated due to potential for loss of virologic response and possible resistance to KALETRA or to the class of protease inhibitors [see Contraindications (4)].
Lipid-modifying agents HMG-CoA Reductase Inhibitors: lovastatin simvastatin atorvastatin rosuvastatin Microsomal triglyceride transfer protein (MTTP) Inhibitor: lomitapide | ↑ lovastatin ↑ simvastatin ↑ atorvastatin ↑ rosuvastatin ↑ lomitapide | Contraindicated due to potential for myopathy including rhabdomyolysis [see Contraindications (4)]. Use atorvastatin with caution and at the lowest necessary dose. Titrate rosuvastatin dose carefully and use the lowest necessary dose; do not exceed rosuvastatin 10 mg/day. Lomitapide is a sensitive substrate for CYP3A4 metabolism. CYP3A4 inhibitors increase the exposure of lomitapide, with strong inhibitors increasing exposure approximately 27-fold. Concomitant use of moderate or strong CYP3A4 inhibitors with lomitapide is contraindicated due to potential for hepatotoxicity [see Contraindications (4)].
Immunosuppressants: e.g. cyclosporine, tacrolimus, sirolimus | ↑ immunosuppressants | Therapeutic concentration monitoring is recommended for immunosuppressant agents when co-administered with KALETRA.
Kinase Inhibitors: fostamatinib (also see anticancer agents above) | ↑ fostamatinib metabolite R406 | Monitor for toxicities of R406 such as hepatotoxicity and neutropenia. Fostamatinib dose reduction may be required.
Long-acting beta-adrenoceptor Agonist: salmeterol | ↑ salmeterol | Concurrent administration of salmeterol and KALETRA is not recommended. The combination may result in increased risk of cardiovascular adverse events associated with salmeterol, including QT prolongation, palpitations and sinus tachycardia.
Narcotic Analgesics: methadone,* fentanyl | ↓ methadone ↑ fentanyl | Dosage of methadone may need to be increased when co-administered with KALETRA. Careful monitoring of therapeutic and adverse effects (including potentially fatal respiratory depression) is recommended when fentanyl is concomitantly administered with KALETRA.
PDE5 inhibitors: avanafil, sildenafil, tadalafil, vardenafil | ↑ avanafil ↑ sildenafil ↑ tadalafil ↑ vardenafil | Sildenafil when used for the treatment of pulmonary arterial hypertension (Revatio®) is contraindicated due to the potential for sildenafil-associated adverse events, including visual abnormalities, hypotension, prolonged erection, and syncope [see Contraindications (4)]. Do not use KALETRA with avanafil because a safe and effective avanafil dosage regimen has not been established. Particular caution should be used when prescribing sildenafil, tadalafil, or vardenafil in patients receiving KALETRA. Co-administration of KALETRA with these drugs may result in an increase in PDE5 inhibitor associated adverse reactions including hypotension, syncope, visual changes and prolonged erection. Use of PDE5 inhibitors for pulmonary arterial hypertension (PAH): Sildenafil (Revatio®) is contraindicated [see Contraindications (4)]. The following dose adjustments are recommended for use of tadalafil (Adcirca®) with KALETRA: Co-administration of ADCIRCA in patients on KALETRA: In patients receiving KALETRA for at least one week, start ADCIRCA at 20 mg once daily. Increase to 40 mg once daily based upon individual tolerability. Co-administration of KALETRA in patients on ADCIRCA: Avoid use of ADCIRCA during the initiation of KALETRA. Stop ADCIRCA at least 24 hours prior to starting KALETRA. After at least one week following the initiation of KALETRA, resume ADCIRCA at 20 mg once daily. Increase to 40 mg once daily based upon individual tolerability. Use of PDE5 inhibitors for erectile dysfunction: It is recommended not to exceed the following doses: • Sildenafil: 25 mg every 48 hours • Tadalafil: 10 mg every 72 hours • Vardenafil: 2.5 mg every 72 hours Use with increased monitoring for adverse events.
Sedative/Hypnotics: triazolam, orally administered midazolam | ↑ triazolam ↑ midazolam | Contraindicated due to potential for prolonged or increased sedation or respiratory depression [see Contraindications (4)].
Sedative/Hypnotics: parenterally administered midazolam | ↑ midazolam | If KALETRA is co-administered with parenteral midazolam, close clinical monitoring for respiratory depression and/or prolonged sedation should be exercised and dosage adjustment should be considered.
Systemic/Inhaled/ Nasal/Ophthalmic Corticosteroids: e.g., betamethasone budesonide ciclesonide dexamethasone fluticasone methylprednisolone mometasone prednisone triamcinolone | ↓ lopinavir ↑ glucocorticoids | Coadministration with oral dexamethasone or other systemic corticosteroids that induce CYP3A may result in loss of therapeutic effect and development of resistance to lopinavir. Consider alternative corticosteroids. Coadministration with corticosteroids whose exposures are significantly increased by strong CYP3A inhibitors can increase the risk for Cushing’s syndrome and adrenal suppression. Alternative corticosteroids including beclomethasone and prednisolone (whose PK and/or PD are less affected by strong CYP3A inhibitors relative to other studied steroids) should be considered, particularly for long-term use.
* see Clinical Pharmacology (12.3) for magnitude of interaction.
# refers to interaction with apalutamide.

7.4 Drugs with No Observed or Predicted Interactions with KALETRA

Drug interaction or clinical studies reveal no clinically significant interaction between KALETRA and desipramine (CYP2D6 probe), etravirine, pitavastatin, pravastatin, stavudine, lamivudine, omeprazole, raltegravir, ranitidine, or rilpivirine.

Based on known metabolic profiles, clinically significant drug interactions are not expected between KALETRA and dapsone, trimethoprim/sulfamethoxazole, azithromycin, erythromycin, or fluconazole.

8 USE IN SPECIFIC POPULATIONS

8.1 Pregnancy

Pregnancy Exposure Registry

There is a pregnancy exposure registry that monitors pregnancy outcomes in women exposed to KALETRA during pregnancy. Physicians are encouraged to register patients by calling the Antiretroviral Pregnancy Registry at 1-800-258-4263.

Risk Summary

Available data from the Antiretroviral Pregnancy Registry show no difference in the risk of overall major birth defects compared to the background rate for major birth defects of 2.7% in the U.S. reference population of the Metropolitan Atlanta Congenital Defects Program (MACDP) (see Data). The estimated background rate of miscarriage in clinically recognized pregnancies in the U.S. general population is 15-20%. The background risk for major birth defects and miscarriage for the indicated population is unknown. Methodological limitations of the APR include the use of MACDP as the external comparator group. The MACDP population is not disease-specific, evaluates women and infants from a limited geographic area, and does not include outcomes for births that occurred at <20 weeks gestation (see Data). No treatment-related malformations were observed when lopinavir in combination with ritonavir was administered to pregnant rats or rabbits; however embryonic and fetal developmental toxicities occurred in rats administered maternally toxic doses.

Clinical Considerations

Dose Adjustments During Pregnancy and the Postpartum Period

Administer 400/100 mg of KALETRA twice daily in pregnant patients with no documented lopinavir-associated resistance substitutions [see Dosage and Administration (2.5) and Clinical Pharmacology (12.3)]. There are insufficient data to recommend KALETRA dosing for pregnant patients with any documented lopinavir-associated resistance substitutions. No dose adjustment of KALETRA is required for patients during the postpartum period.

Once daily KALETRA dosing is not recommended in pregnancy.

Avoid use of KALETRA oral solution during pregnancy due to the ethanol content. KALETRA oral solution contains the excipients ethanol, approximately 42% (v/v and propylene glycol, approximately 15%.

Data

Human Data

KALETRA was evaluated in 12 HIV-infected pregnant women in an open-label pharmacokinetic trial [see Clinical Pharmacology (12.3)]. No new trends in the safety profile were identified in pregnant women dosed with KALETRA compared to the safety described in non-pregnant adults, based on the review of these limited data.

Antiretroviral Pregnancy Registry Data: Based on prospective reports from the Antiretroviral Pregnancy Registry (APR) of over 3,000 exposures to lopinavir containing regimens (including over 1,000 exposed in the first trimester), there was no difference between lopinavir and overall birth defects compared with the background birth defect rate of 2.7% in the U.S. reference population of the Metropolitan Atlanta Congenital Defects Program. The prevalence of birth defects in live births was 2.1% (95% CI: 1.4%-3.0%) following first-trimester exposure to lopinavir-containing regimens and 3.0% (95% CI: 2.4%-3.8%) following second and third trimester exposure to lopinavir-containing regimens. Based on prospective reports from the APR of over 5,000 exposures to ritonavir containing regimens (including over 2,000 exposures in the first trimester) there was no difference between ritonavir and overall birth defects compared with the U.S. background rate (MACDP). The prevalence of birth defects in live births was 2.2% (95% CI: 1.7%-2.8%) following first-trimester exposure to ritonavir-containing regimens and 2.9% (95% CI: 2.4%-3.6%) following second and third trimester exposure to ritonavir-containing regimens. For both lopinavir and ritonavir, sufficient numbers of first trimester exposures have been monitored to detect at least a 1.5 fold increase in risk of overall birth defects and a 2 fold increase in risk of birth defects in the cardiovascular and genitourinary systems.

Animal Data

Embryonic and fetal developmental toxicities (early resorption, decreased fetal viability, decreased fetal body weight, increased incidence of skeletal variations and skeletal ossification delays) occurred in rats administered lopinavir in combination with ritonavir (on gestation days 6-17) at a maternally toxic dosage. Based on AUC measurements, the drug exposures in rats at the toxic doses were approximately 0.7 times (for lopinavir) and 1.8 times (for ritonavir) the exposures in humans at the recommended therapeutic dose (400/100 mg twice daily). In a pre- and post-natal study in rats, a developmental toxicity (a decrease in survival in pups between birth and postnatal Day 21) occurred.

No embryonic and fetal developmental toxicities were observed in rabbits administered lopinavir in combination with ritonavir (on gestation days 6-18) at a maternally toxic dosage. Based on AUC measurements, the drug exposures in rabbits at the toxic doses were approximately 0.6 times (for lopinavir) and similar to (for ritonavir) the exposures in humans at the recommended therapeutic dose (400/100 mg twice daily).

8.2 Lactation

Risk Summary

The Centers for Disease Control and Prevention recommend that HIV-1 infected mothers not breastfeed their infants to avoid risking postnatal transmission of HIV-1. Because of the potential for: 1) HIV transmission (in HIV-negative infants), 2) developing viral resistance (in HIV- positive infants), and 3) adverse reactions in the breastfed infant, instruct mothers not to breastfeed if they are receiving KALETRA.

8.3 Females and Males of Reproductive Potential

Contraception

Use of KALETRA may reduce the efficacy of combined hormonal contraceptives. Advise patients using combined hormonal contraceptives to use an effective alternative contraceptive method or an additional barrier method of contraception [see Drug Interactions (7.3)].

8.4 Pediatric Use

The safety, efficacy, and pharmacokinetic profiles of KALETRA in pediatric patients below the age of 14 days have not been established. KALETRA should not be administered once daily in pediatric patients.

An open-label, multi-center, dose-finding trial was performed to evaluate the pharmacokinetic profile, tolerability, safety and efficacy of KALETRA oral solution containing lopinavir 80 mg/mL and ritonavir 20 mg/mL at a dose of 300/75 mg/m^2 twice daily plus two NRTIs in HIV-infected infants ≥14 days and < 6 months of age. Results revealed that infants younger than 6 months of age generally had lower lopinavir AUC12 than older children (6 months to 12 years of age), however, despite the lower lopinavir drug exposure observed, antiviral activity was demonstrated as reflected in the proportion of subjects who achieved HIV-1 RNA <400 copies/mL at Week 24 [see Adverse Reactions (6.2), Clinical Pharmacology (12.3), Clinical Studies (14.4)].

Safety and efficacy in pediatric patients > 6 months of age was demonstrated in a clinical trial in 100 patients. The clinical trial was an open-label, multicenter trial evaluating the pharmacokinetic profile, tolerability, safety, and efficacy of KALETRA oral solution containing lopinavir 80 mg/mL and ritonavir 20 mg/mL in 100 antiretroviral naïve and experienced pediatric patients ages 6 months to 12 years. Dose selection for patients 6 months to 12 years of age was based on the following results. The 230/57.5 mg/m^2 oral solution twice daily regimen without nevirapine and the 300/75 mg/m^2 oral solution twice daily regimen with nevirapine provided lopinavir plasma concentrations similar to those obtained in adult patients receiving the 400/100 mg twice daily regimen (without nevirapine) [see Adverse Reactions (6.2), Clinical Pharmacology (12.3), Clinical Studies (14.4)].

A prospective multicenter, open-label trial evaluated the pharmacokinetic profile, tolerability, safety and efficacy of high-dose KALETRA with or without concurrent NNRTI therapy (Group 1: 400/100 mg/m^2 twice daily + ≥ 2 NRTIs; Group 2: 480/120 mg/m^2 twice daily + ≥ 1 NRTI + 1 NNRTI) in 26 children and adolescents ≥ 2 years to < 18 years of age who had failed prior therapy. Patients also had saquinavir mesylate added to their regimen. This strategy was intended to assess whether higher than approved doses of KALETRA could overcome protease inhibitor cross-resistance. High doses of KALETRA exhibited a safety profile similar to those observed in previous trials; changes in HIV-1 RNA were less than anticipated; three patients had HIV-1 RNA <400 copies/mL at Week 48. CD4+ cell count increases were noted in the eight patients who remained on treatment for 48 weeks [see Adverse Reactions (6.2), Clinical Pharmacology (12.3)].

A prospective multicenter, randomized, open-label study evaluated the efficacy and safety of twice-daily versus once-daily dosing of KALETRA tablets dosed by weight as part of combination antiretroviral therapy (cART) in virologically suppressed HIV-1 infected children (n=173). Children were eligible when they were aged < 18 years, ≥ 15 kg in weight, receiving cART that included KALETRA, HIV-1 ribonucleic acid (RNA) < 50 copies/mL for at least 24 weeks and able to swallow tablets. At week 24, efficacy (defined as the proportion of subjects with plasma HIV-1 RNA less than 50 copies per mL) was significantly higher in subjects receiving twice daily dosing compared to subjects receiving once daily dosing. The safety profile was similar between the two treatment arms although there was a greater incidence of diarrhea in the once daily treated subjects.

8.5 Geriatric Use

Clinical studies of KALETRA did not include sufficient numbers of subjects aged 65 and over to determine whether they respond differently from younger subjects. In general, appropriate caution should be exercised in the administration and monitoring of KALETRA in elderly patients reflecting the greater frequency of decreased hepatic, renal, or cardiac function, and of concomitant disease or other drug therapy.

8.6 Hepatic Impairment

KALETRA is principally metabolized by the liver; therefore, caution should be exercised when administering this drug to patients with hepatic impairment, because lopinavir concentrations may be increased [see Warnings and Precautions (5.4) and Clinical Pharmacology (12.3)].

10 OVERDOSAGE

Overdoses with KALETRA oral solution have been reported. One of these reports described fatal cardiogenic shock in a 2.1 kg infant who received a single dose of 6.5 mL of KALETRA oral solution (520 mg lopinavir, approximately 10-fold above the recommended lopinavir dose) nine days prior. The following events have been reported in association with unintended overdoses in preterm neonates: complete AV block, cardiomyopathy, lactic acidosis, and acute renal failure [see Warnings and Precautions (5.2)]. Healthcare professionals should be aware that KALETRA oral solution is highly concentrated and therefore, should pay special attention to accurate calculation of the dose of KALETRA, transcription of the medication order, dispensing information and dosing instructions to minimize the risk for medication errors and overdose. This is especially important for infants and young children.

KALETRA oral solution contains approximately 42% (v/v) ethanol and approximately 15% (w/v) propylene glycol. Ingestion of the product over the recommended dose by an infant or a young child could result in significant toxicity and could potentially be lethal.

Human experience of acute overdosage with KALETRA is limited. Treatment of overdose with KALETRA should consist of general supportive measures including monitoring of vital signs and observation of the clinical status of the patient. There is no specific antidote for overdose with KALETRA. If indicated, elimination of unabsorbed drug should be achieved by gastric lavage. Administration of activated charcoal may also be used to aid in removal of unabsorbed drug. Since lopinavir is highly protein bound, dialysis is unlikely to be beneficial in significant removal of the drug. However, dialysis can remove both ethanol and propylene glycol in the case of overdose with KALETRA oral solution.

11 DESCRIPTION

KALETRA is a co-formulation of lopinavir and ritonavir. Lopinavir is an inhibitor of the HIV-1 protease. As co-formulated in KALETRA, ritonavir inhibits the CYP3A-mediated metabolism of lopinavir, thereby providing increased plasma levels of lopinavir.

Lopinavir is chemically designated as [1S-[1R*,(R*), 3R*, 4R*]]-N-[4-[[(2,6-dimethylphenoxy)acetyl]amino]-3-hydroxy-5-phenyl-1-(phenylmethyl)pentyl]tetrahydro-alpha-(1-methylethyl)-2-oxo-1(2H)-pyrimidineacetamide. Its molecular formula is C37H48N4O5, and its molecular weight is 628.80. Lopinavir is a white to light tan powder. It is freely soluble in methanol and ethanol, soluble in isopropanol and practically insoluble in water. Lopinavir has the following structural formula:

Ritonavir is chemically designated as 10-hydroxy-2-methyl-5-(1-methylethyl)-1- [2-(1-methylethyl)-4-thiazolyl]-3,6-dioxo-8,11-bis(phenylmethyl)-2,4,7,12-tetraazatridecan-13-oic acid, 5-thiazolylmethyl ester, [5S-(5R*,8R*,10R*,11R*)]. Its molecular formula is C37H48N6O5S2, and its molecular weight is 720.95. Ritonavir is a white to light tan powder. It is freely soluble in methanol and ethanol, soluble in isopropanol and practically insoluble in water. Ritonavir has the following structural formula:

KALETRA tablets are available for oral administration in two strengths:

- Yellow or red tablets containing 200 mg of lopinavir and 50 mg of ritonavir
- Pale yellow or pink tablets containing 100 mg of lopinavir and 25 mg of ritonavir.

The yellow, 200 mg lopinavir and 50 mg ritonavir, tablets contain the following inactive ingredients: colloidal silicon dioxide, copovidone, sodium stearyl fumarate and sorbitan monolaurate. The following are the ingredients in the film coating: colloidal silicon dioxide, hydroxypropyl cellulose, hypromellose, polyethylene glycol 400, polyethylene glycol 3350, polysorbate 80, talc, titanium dioxide, and yellow ferric oxide E172.

The red, 200 mg lopinavir and 50 mg ritonavir, tablets contain the following inactive ingredients: colloidal silicon dioxide, copovidone, sodium stearyl fumarate and sorbitan monolaurate. The following are the ingredients in the film coating: colloidal silicon dioxide, hydroxypropyl cellulose, hypromellose, polyethylene glycol 400, polyethylene glycol 3350, polysorbate 80, talc, titanium dioxide, and red ferric oxide E172.

The pale yellow, 100 mg lopinavir and 25 mg ritonavir, tablets contain the following inactive ingredients: colloidal silicon dioxide, copovidone, sodium stearyl fumarate, and sorbitan monolaurate. The following are the ingredients in the film coating: polyethylene glycol 3350, polyvinyl alcohol, talc, titanium dioxide, and yellow ferric oxide E172.

The pink, 100 mg lopinavir and 25 mg ritonavir, tablets contain the following inactive ingredients: colloidal silicon dioxide, copovidone, sodium stearyl fumarate, and sorbitan monolaurate. The following are the ingredients in the film coating: polyethylene glycol 3350, polyvinyl alcohol, talc, titanium dioxide, and red ferric oxide E172.

KALETRA oral solution is available for oral administration as 80 mg lopinavir and 20 mg ritonavir per milliliter with the following inactive ingredients: acesulfame potassium, artificial cotton candy flavor, citric acid, ethanol, glycerin, high fructose corn syrup, Magnasweet-110 flavor, menthol, natural & artificial vanilla flavor, peppermint oil, polyoxyl 40 hydrogenated castor oil, povidone, propylene glycol, saccharin sodium, sodium chloride, sodium citrate, and water.

KALETRA oral solution contains approximately 42% (v/v) ethanol and approximately 15% (w/v) propylene glycol.

12 CLINICAL PHARMACOLOGY

12.1 Mechanism of Action

KALETRA is a fixed-dose combination of HIV-1 antiviral drugs lopinavir [see Microbiology (12.4)] and ritonavir. As co-formulated in KALETRA, ritonavir inhibits the CYP3A-mediated metabolism of lopinavir, thereby providing increased plasma levels of lopinavir.

12.2 Pharmacodynamics

Cardiac Electrophysiology

The effect of KALETRA on QTcF interval was evaluated in a placebo and active (moxifloxacin 400 mg once daily) controlled crossover study in 39 healthy adults. The maximum mean time-matched (95% upper confidence bound) differences in QTcF interval from placebo after baseline-correction were 5.3 (8.1) and 15.2 (18.0) mseconds (msec) for 400/100 mg twice daily and supratherapeutic 800/200 mg twice daily KALETRA, respectively. KALETRA 800/200 mg twice daily resulted in a Day 3 mean Cmax approximately 2-fold higher than the mean Cmax observed with the approved once daily and twice daily KALETRA doses at steady state. The maximum mean (95% upper confidence bound) difference from placebo in the PR interval after baseline-correction were 24.9 (21.5, 28.3) and 31.9 (28.5, 35.3) msec for 400/100 mg twice daily and supratherapeutic 800/200 mg twice daily KALETRA, respectively [see Warnings and Precautions (5.5, 5.6)].

12.3 Pharmacokinetics

The pharmacokinetic properties of lopinavir are summarized in Table 13. The steady-state pharmacokinetic parameters of lopinavir are summarized in Table 14. Under fed conditions, lopinavir concentrations were similar following administration of KALETRA tablets to capsules with less pharmacokinetic variability. Under fed conditions (500 kcal, 25% from fat), lopinavir concentrations were similar following administration of KALETRA capsules and oral solution.

Table 13. Pharmacokinetic Properties of Lopinavir

Absorption
Tmax (hr)a | 4.4 ± 0.8
Effect of meal (relative to fasting) Tablet Oral solution | ↑ 19%b ↑ 130%b
Distribution
% Bound to human plasma proteins | > 98
Vd/Fa (L) | 16.9
Metabolism
Metabolism | CYP3A
Elimination
Major route of elimination | hepatic
t1/2 (h)a | 6.9 ± 2.2
% of dose excreted in urine | 10.4 ± 2.3
% of dose excreted in feces | 82.6 ± 2.5
a. Kaletra tablet
b. Changes in AUC values

Table 14. Steady-State Pharmacokinetic Parameters of Lopinavir, Mean ± SD

Pharmacokinetic Parameter | Twice Dailya | Once Dailyb
Cmax (µg/mL) | 9.8 ± 3.7 | 11.8 ± 3.7
Cmin (µg/mL) | 5.5 ± 2.7 | 1.7 ± 1.6
AUCtau (µg•h/mL) | 92.6 ± 36.7 | 154.1 ± 61.4
1. 19 HIV-1 subjects, Kaletra 400/100 mg twice daily
2. 24 HIV-1 subjects, Kaletra 800/200 mg + emtricitabine 200 mg + tenofovir DF 300 mg

Specific Populations

Gender, Race and Age

No gender or race related pharmacokinetic differences have been observed in adult patients. Lopinavir pharmacokinetics have not been studied in elderly patients.

Pediatric Patients

The 230/57.5 mg/m^2 twice daily regimen without nevirapine and the 300/75 mg/m^2 twice daily regimen with nevirapine provided lopinavir plasma concentrations similar to those obtained in adult patients receiving the 400/100 mg twice daily regimen without nevirapine.

Table 15. Lopinavir Pharmacokinetic Data from Pediatric Clinical Trials, Mean ± SD

Cmax (μg/mL) | Cmin (μg/mL) | AUC 12 (μg•hr/m)
Age ≥ 14 Days to < 6 Weeks Cohort (N = 9):
5.17 ± 1.84a | 1.40 ± 0.48a | 43.39 ± 14.80a
Age ≥ 6 Weeks to < 6 Months Cohort (N = 18):
9.39 ± 4.91a | 1.95 ± 1.80a | 74.50 ± 37.87a
Age ≥ 6 Months to ≤ 12 years Cohort (N = 24):
8.2 ± 2.9b | 3.4 ± 2.1b | 72.6 ± 31.1b
10.0 ± 3.3c | 3.6 ± 3.5c | 85.8 ± 36.9c
1. KALETRA oral solution300/75 mg/m^2 twice daily without concomitant NNRTI therapy
2. KALETRA oral solution 230/57.5 mg/m^2 twice daily without nevirapine (n=12)
3. KALETRA oral solution 300/75 mg/m^2 twice daily with nevirapine (n=12)

Pregnancy

The C12h values of lopinavir were lower during the second and third trimester by approximately 40% as compared to post-partum in 12 HIV-infected pregnant women received KALETRA 400 mg/100 mg twice daily. Yet this decrease is not considered clinically relevant in patients with no documented KALETRA-associated resistance substitutions receiving 400 mg/100 mg twice daily [see Use in Specific Populations (8.1)].

Renal Impairment

Lopinavir pharmacokinetics have not been studied in patients with renal impairment; however, since the renal clearance of lopinavir is negligible, a decrease in total body clearance is not expected in patients with renal impairment.

Hepatic Impairment

Multiple dosing of KALETRA 400/100 mg twice daily to HIV-1 and HCV co-infected patients with mild to moderate hepatic impairment (n = 12) resulted in a 30% increase in lopinavir AUC and 20% increase in Cmax compared to HIV-1 infected subjects with normal hepatic function (n = 12). Additionally, the plasma protein binding of lopinavir was statistically significantly lower in both mild and moderate hepatic impairment compared to controls (99.09 vs. 99.31%, respectively). KALETRA has not been studied in patients with severe hepatic impairment [see Warnings and Precautions (5.4) and Use in Specific Populations (8.6)].

Drug Interactions

KALETRA is an inhibitor of the P450 isoform CYP3A in vitro. KALETRA does not inhibit CYP2D6, CYP2C9, CYP2C19, CYP2E1, CYP2B6 or CYP1A2 at clinically relevant concentrations.

KALETRA has been shown in vivo to induce its own metabolism and to increase the biotransformation of some drugs metabolized by cytochrome P450 enzymes and by glucuronidation.

The effects of co-administration of KALETRA on the AUC, Cmax and Cmin are summarized in Table 16 (effect of other drugs on lopinavir) and Table 17 (effect of KALETRA on other drugs). For information regarding clinical recommendations, see Table 12 in Drug Interactions (7).

Table 16. Drug Interactions: Pharmacokinetic Parameters for Lopinavir in the Presence of the Co-administered Drug for Recommended Alterations in Dose or Regimen

Co- administered Drug | Dose of Co- administered Drug (mg) | Dose of KALETRA (mg) | n | Ratio (in combination with Co-administered drug/alone) of Lopinavir Pharmacokinetic Parameters (90% CI); No Effect = 1.00
 |  |  |  | Cmax | AUC | Cmin
Efavirenz^1 | 600 at bedtime | 400/100 capsule twice daily | 11, 7^3 | 0.97 (0.78, 1.22) | 0.81 (0.64, 1.03) | 0.61 (0.38, 0.97)
 | 600 at bedtime | 500/125 tablet twice daily | 19 | 1.12 (1.02, 1.23) | 1.06 (0.96, 1.17) | 0.90 (0.78, 1.04)
 | 600 at bedtime | 600/150 tablet twice daily | 23 | 1.36 (1.28, 1.44) | 1.36 (1.28, 1.44) | 1.32 (1.21, 1.44)
Etravirine | 200 twice daily | 400/100 mg twice day (tablets) | 16 | 0.89 (0.82-0.96) | 0.87 (0.83-0.92) | 0.80 (0.73-0.88)
Fosamprenavir^2 | 700 twice daily plus ritonavir 100 twice daily | 400/100 capsule twice daily | 18 | 1.30 (0.85, 1.47) | 1.37 (0.80, 1.55) | 1.52 (0.72, 1.82)
Ketoconazole | 200 single dose | 400/100 capsule twice daily | 12 | 0.89 (0.80, 0.99) | 0.87 (0.75, 1.00) | 0.75 (0.55, 1.00)
Nelfinavir | 1000 twice daily | 400/100 capsule twice daily | 13 | 0.79 (0.70, 0.89) | 0.73 (0.63, 0.85) | 0.62 (0.49, 0.78)
Nevirapine | 200 twice daily steady-state | 400/100 capsule twice daily | 22, 19^3 | 0.81 (0.62, 1.05) | 0.73 (0.53, 0.98) | 0.49 (0.28, 0.74)
 | 7 mg/kg or 4 mg/kg once daily; twice daily 1 wk^5 | (> 1 yr) 300/ 75 mg/m^2 oral solution twice daily | 12, 15^3 | 0.86 (0.64, 1.16) | 0.78 (0.56, 1.09) | 0.45 (0.25, 0.81)
Ombitasvir/ paritaprevir/ ritonavir+ dasabuvir^2 | 25/150/100 + dasabuvir 400 | 400/100 tablet twice daily | 6 | 0.87 (0.76, 0.99) | 0.94 (0.81, 1.10) | 1.15 (0.93, 1.42)
Omeprazole | 40 once daily, 5 d | 400/100 tablet twice daily, 10 d | 12 | 1.08 (0.99, 1.17) | 1.07 (0.99, 1.15) | 1.03 (0.90, 1.18)
 | 40 once daily, 5 d | 800/200 tablet once daily, 10 d | 12 | 0.94 (0.88, 1.00) | 0.92 (0.86, 0.99) | 0.71 (0.57, 0.89)
Pravastatin | 20 once daily, 4 d | 400/100 capsule twice daily, 14 d | 12 | 0.98 (0.89, 1.08) | 0.95 (0.85, 1.05) | 0.88 (0.77, 1.02)
Ranitidine | 150 single dose | 400/100 tablet twice daily, 10 d | 12 | 0.99 (0.95, 1.03) | 0.97 (0.93, 1.01) | 0.90 (0.85, 0.95)
 | 150 single dose | 800/200 tablet once daily, 10 d | 10 | 0.97 (0.95, 1.00) | 0.95 (0.91, 0.99) | 0.82 (0.74, 0.91)
Rifabutin | 150 once daily | 400/100 capsule twice daily | 14 | 1.08 (0.97, 1.19) | 1.17 (1.04, 1.31) | 1.20 (0.96, 1.65)
Rifampin | 600 once daily | 400/100 capsule twice daily | 22 | 0.45 (0.40, 0.51) | 0.25 (0.21, 0.29) | 0.01 (0.01, 0.02)
 | 600 once daily | 800/200 capsule twice daily | 10 | 1.02 (0.85, 1.23) | 0.84 (0.64, 1.10) | 0.43 (0.19, 0.96)
 | 600 once daily | 400/400 capsule twice daily | 9 | 0.93 (0.81, 1.07) | 0.98 (0.81, 1.17) | 1.03 (0.68, 1.56)
Rilpivirine | 150 once daily | 400/100 twice daily (capsules) | 15 | 0.96 (0.88-1.05) | 0.99 (0.89-1.10) | 0.89 (0.73-1.08)
Ritonavir | 100 twice daily | 400/100 capsule twice daily | 8, 21^3 | 1.28 (0.94, 1.76) | 1.46 (1.04, 2.06) | 2.16 (1.29, 3.62)
Tipranavir/ ritonavir | 500/200 twice daily | 400/100 capsule twice daily | 21 69^3 | 0.53 (0.40, 0.69) | 0.45 (0.32, 0.63) | 0.30 (0.17, 0.51) 0.48^4 (0.40, 0.58)
1 Reference for comparison is lopinavir/ritonavir 400/100 mg twice daily without efavirenz.
2 Data extracted from the U.S. prescribing information of co-administered drugs.
3 Parallel group design
4 Drug levels obtained at 8-16 hours post dose
N/A = Not available.

Table 17. Drug Interactions: Pharmacokinetic Parameters for Co-administered Drug in the Presence of KALETRA for Recommended Alterations in Dose or Regimen

Co- administered Drug | Dose of Co- administered Drug (mg) | Dose of KALETRA (mg) | n | Ratio (in combination with KALETRA/alone) of Co- administered Drug Pharmacokinetic Parameters (90% CI); No Effect = 1.00
 |  |  |  | Cmax | AUC | Cmin
Bedaquiline^1 | 400 single dose | 400/100 twice daily | N/A | N/A | 1.22 (1.11, 1.34) | N/A
Efavirenz | 600 at bedtime | 400/100 capsule twice daily | 11, 12^3 | 0.91 (0.72, 1.15) | 0.84 (0.62, 1.15) | 0.84 (0.58, 1.20)
Elbasvir/ grazoprevir^1 | 50 once daily | 400/100 twice daily | 10 | 2.87 (2.29, 3.58) | 3.71 (3.05, 4.53) | 4.58 (3.72, 5.64)
 | 200 once daily |  | 13 | 7.31 (5.65, 9.45) | 12.86 (10.25, 16.13) | 21.70 (12.99, 36.25)
Ethinyl Estradiol | 35 µg once daily (Ortho Novum®) | 400/100 capsule twice daily | 12 | 0.59 (0.52, 0.66) | 0.58 (0.54, 0.62) | 0.42 (0.36, 0.49)
Etravirine | 200 twice daily | 400/100 tablet twice day | 16 | 0.70 (0.64-0.78) | 0.65 (0.59-0.71) | 0.55 (0.49-0.62)
Fosamprenavir^1 | 700 twice daily plus ritonavir 100 twice daily | 400/100 capsule twice daily | 18 | 0.42 (0.30, 0.58) | 0.37 (0.28, 0.49) | 0.35 (0.27, 0.46)
Indinavir | 600 twice daily combo nonfasting vs. 800 three times daily alone fasting | 400/100 capsule twice daily | 13 | 0.71 (0.63, 0.81) | 0.91 (0.75, 1.10) | 3.47 (2.60, 4.64)
Ketoconazole | 200 single dose | 400/100 capsule twice daily | 12 | 1.13 (0.91, 1.40) | 3.04 (2.44, 3.79) | N/A
Maraviroc^1 | 300 twice daily | 400/100 twice daily | 11 | 1.97 (1.66, 2.34) | 3.95 (3.43, 4.56) | 9.24 (7.98, 10.7)
Methadone | 5 single dose | 400/100 capsule twice daily | 11 | 0.55 (0.48, 0.64) | 0.47 (0.42, 0.53) | N/A
Nelfinavir | 1000 twice daily combo vs. 1250 twice daily alone | 400/100 capsule twice daily | 13 | 0.93 (0.82, 1.05) | 1.07 (0.95, 1.19) | 1.86 (1.57, 2.22)
M8 metabolite |  |  |  | 2.36 (1.91, 2.91) | 3.46 (2.78, 4.31) | 7.49 (5.85, 9.58)
Nevirapine | 200 once daily twice daily | 400/100 capsule twice daily | 5, 6^3 | 1.05 (0.72, 1.52) | 1.08 (0.72, 1.64) | 1.15 (0.71, 1.86)
Norethindrone | 1 once daily (Ortho Novum®) | 400/100 capsule twice daily | 12 | 0.84 (0.75, 0.94) | 0.83 (0.73, 0.94) | 0.68 (0.54, 0.85)
Ombitasvir/ paritaprevir/ ritonavir+ dasabuvir^1 | 25/150/100 + dasabuvir 400 | 400/100 tablet twice daily | 6 | 1.14 (1.01, 1.28) | 1.17 (1.07, 1.28) | 1.24 (1.14, 1.34)
 |  |  |  | 2.04 (1.30, 3.20) | 2.17 (1.63, 2.89) | 2.36 (1.00, 5.55)
 |  |  |  | 1.55 (1.16, 2.09) | 2.05 (1.49, 2.81) | 5.25 (3.33, 8.28)
 |  |  |  | 0.99 (0.75, 1.31) | 0.93 (0.75, 1.15) | 0.68 (0.57, 0.80)
Pitavastatin^1 | 4 once daily | 400/100 tablet twice daily | 23 | 0.96 (0.84-1.10) | 0.80 (0.73-0.87) | N/A
Pravastatin | 20 once daily | 400/100 capsule twice daily | 12 | 1.26 (0.87, 1.83) | 1.33 (0.91, 1.94) | N/A
Rifabutin | 150 once daily combo vs. 300 once daily alone | 400/100 capsule twice daily | 12 | 2.12 (1.89, 2.38) | 3.03 (2.79, 3.30) | 4.90 (3.18, 5.76)
25-O-desacetyl rifabutin |  |  |  | 23.6 (13.7, 25.3) | 47.5 (29.3, 51.8) | 94.9 (74.0, 122)
Rifabutin + 25- O-desacetyl rifabutin |  |  |  | 3.46 (3.07, 3.91) | 5.73 (5.08, 6.46) | 9.53 (7.56, 12.01)
Rilpivirine | 150 once daily | 400/100 capsules twice daily | 15 | 1.29 (1.18-1.40) | 1.52 (1.36-1.70) | 1.74 (1.46-2.08)
Rosuvastatin^2 | 20 once daily | 400/100 tablet twice daily | 15 | 4.66 (3.4, 6.4) | 2.08 (1.66, 2.6) | 1.04 (0.9, 1.2)
Tenofovir alafenamide^1 | 10 once daily | 800/200 tablet once daily | 10 | 2.19 (1.72, 2.79) | 1.47 (1.17, 1.85) | N/A
Tenofovir disoproxil fumarate^1 | 300 once daily | 400/100 capsule twice daily | 24 | No Change | 1.32 (1.26, 1.38) | 1.51 (1.32, 1.66)
1 Data extracted from the U.S. prescribing information of co-administered drugs.
2 Kiser, et al. J Acquir Immune Defic Syndr. 2008 Apr 15; 47(5):570-8.
3 Parallel group design
N/A = Not available.

12.4 Microbiology

Mechanism of Action

Lopinavir, an inhibitor of the HIV-1 protease, prevents cleavage of the viral Gag-Pol polyprotein, resulting in the production of immature, non-infectious viral particles.

Antiviral Activity

In the absence of human serum, the mean 50% effective concentration (EC50) values of lopinavir against five different HIV-1 subtype B laboratory strains in lymphoblastic cell lines ranged from 10-27 nM (0.006-0.017 µg/mL, 1 µg/mL = 1.6 µM), and ranged from 4-11 nM (0.003-0.007 µg/mL) against several HIV-1 subtype B clinical isolates in peripheral blood lymphocytes (n = 6). In the presence of 50% human serum, the mean EC50 values of lopinavir against these five HIV-1 laboratory strains ranged from 65-289 nM (0.04-0.18 µg/mL), representing a 7 to 11-fold attenuation. The EC50 values of lopinavir against three different HIV-2 strains ranged from 12-180 nM (0.008-113 μg/mL).

Resistance

HIV-1 isolates with reduced susceptibility to lopinavir have been selected in cell culture. The presence of ritonavir does not appear to influence the selection of lopinavir-resistant viruses in cell culture.

In a study of 653 antiretroviral treatment-naïve patients (Study 863), plasma viral isolates from each patient on treatment with plasma HIV-1 RNA >400 copies/mL at Week 24, 32, 40 and/or 48 were analyzed. No specific amino acid substitutions could be associated with resistance to KALETRA in the virus from 37 evaluable KALETRA-treated patients. The selection of resistance to KALETRA in antiretroviral treatment-naïve pediatric patients (Study 940) appears to be consistent with that seen in adult patients (Study 863).

Resistance to KALETRA has been noted to emerge in patients treated with other protease inhibitors prior to KALETRA therapy. In studies of 227 antiretroviral treatment-naïve and protease inhibitor experienced patients, isolates from 4 of 23 patients with quantifiable (>400 copies/mL) viral RNA following treatment with KALETRA for 12 to 100 weeks displayed significantly reduced susceptibility to lopinavir compared to the corresponding baseline viral isolates. All four of these patients had previously received treatment with at least one protease inhibitor and had at least 4 substitutions associated with protease inhibitor resistance immediately prior to KALETRA therapy. Following viral rebound, isolates from these patients all contained additional substitutions, some of which are recognized to be associated with protease inhibitor resistance.

Cross-resistance - Nonclinical Studies

Varying degrees of cross-resistance have been observed among HIV-1 protease inhibitors. The antiviral activity in cell culture of lopinavir against clinical isolates from patients previously treated with a single protease inhibitor was determined (Table 18).

Table 18. Susceptibility Reduction to Lopinavir Against Isolates from Patients Previously Treated With a Single Protease Inhibitor

Susceptibility reduced by >4 fold | Susceptibility reduced to LPV
Indinavir (n=16) | 5.7 fold
Nelfinavir (n=13) | <4 fold
Ritonavir (n=3) | 8.32 fold
Saquinavir (n=4) | <4 fold

Isolates from patients previously treated with two or more protease inhibitors showed greater reductions in susceptibility to lopinavir, as described in the following section.

Clinical Studies - Antiviral Activity of KALETRA in Patients with Previous Protease Inhibitor Therapies

The clinical relevance of reduced susceptibility in cell culture to lopinavir has been examined by assessing the virologic response to KALETRA therapy in treatment-experienced patients, with respect to baseline viral genotype in three studies and baseline viral phenotype in one study.

Virologic response to KALETRA has been shown to be affected by the presence of three or more of the following amino acid substitutions in protease at baseline: L10F/I/R/V, K20M/N/R, L24I, L33F, M36I, I47V, G48V, I54L/T/V, V82A/C/F/S/T, and I84V. Table 19 shows the 48-week virologic response (HIV-1 RNA <400 copies/mL) according to the number of the above protease inhibitor resistance-associated substitutions at baseline in studies 888 and 765 [see Clinical Studies (14.2) and (14.3)] and study 957 (see below). Once daily administration of KALETRA for adult patients with three or more of the above substitutions is not recommended.

Table 19. Virologic Response (HIV-1 RNA <400 copies/mL) at Week 48 by Baseline KALETRA Susceptibility and by Number of Protease Substitutions Associated with Reduced Response to KALETRA^1

Number of protease inhibitor substitutions at baseline^1 | Study 888 (Single protease inhibitor-experienced^2, NNRTI-naïve) n=130 | Study 765 (Single protease inhibitor-experienced^3, NNRTI-naïve) n=56 | Study 957 (Multiple protease inhibitor-experienced^4, NNRTI-naïve) n=50
0-2 | 76/103 (74%) | 34/45 (76%) | 19/20 (95%)
3-5 | 13/26 (50%) | 8/11 (73%) | 18/26 (69%)
6 or more | 0/1 (0%) | N/A | 1/4 (25%)
1 Substitutions considered in the analysis included L10F/I/R/V, K20M/N/R, L24I, L33F, M36I, I47V, G48V, I54L/T/V, V82A/C/F/S/T, and I84V.
2 43% indinavir, 42% nelfinavir, 10% ritonavir, 15% saquinavir.
3 41% indinavir, 38% nelfinavir, 4% ritonavir, 16% saquinavir.
4 86% indinavir, 54% nelfinavir, 80% ritonavir, 70% saquinavir.

Virologic response to KALETRA therapy with respect to phenotypic susceptibility to lopinavir at baseline was examined in Study 957. In this study 56 NNRTI-naïve patients with HIV-1 RNA >1,000 copies/mL despite previous therapy with at least two protease inhibitors selected from indinavir, nelfinavir, ritonavir, and saquinavir were randomized to receive one of two doses of KALETRA in combination with efavirenz and nucleoside reverse transcriptase inhibitors (NRTIs). The EC50 values of lopinavir against the 56 baseline viral isolates ranged from 0.5- to 96-fold the wild-type EC50 value. Fifty-five percent (31/56) of these baseline isolates displayed >4-fold reduced susceptibility to lopinavir. These 31 isolates had a median reduction in lopinavir susceptibility of 18-fold. Response to therapy by baseline lopinavir susceptibility is shown in Table 20.

Table 20. HIV-1 RNA Response at Week 48 by Baseline Lopinavir Susceptibility^1

Lopinavir susceptibility^2 at baseline | HIV-1 RNA <400 copies/mL (%) | HIV-1 RNA <50 copies/mL (%)
< 10 fold | 25/27 (93%) | 22/27 (81%)
> 10 and < 40 fold | 11/15 (73%) | 9/15 (60%)
≥ 40 fold | 2/8 (25%) | 2/8 (25%)
1 Lopinavir susceptibility was determined by recombinant phenotypic technology performed by Virologic.
2 Fold change in susceptibility from wild type.

13 NONCLINICAL TOXICOLOGY

13.1 Carcinogenesis, Mutagenesis, Impairment of Fertility

Carcinogenesis

Lopinavir/ritonavir combination was evaluated for carcinogenic potential by oral gavage administration to mice and rats for up to 104 weeks. Results showed an increase in the incidence of benign hepatocellular adenomas and an increase in the combined incidence of hepatocellular adenomas plus carcinoma in both males and females in mice and males in rats at doses that produced approximately 1.6-2.2 times (mice) and 0.5 times (rats) the human exposure (based on AUC0-24hr measurement) at the recommended dose of 400/100 mg KALETRA twice daily. Administration of lopinavir/ritonavir did not cause a statistically significant increase in the incidence of any other benign or malignant neoplasm in mice or rats.

Carcinogenicity studies in mice and rats have been carried out on ritonavir. In male mice, there was a dose dependent increase in the incidence of both adenomas and combined adenomas and carcinomas in the liver. Based on AUC measurements, the exposure at the high dose was approximately 4-fold for males that of the exposure in humans with the recommended therapeutic dose (400/100 mg KALETRA twice daily). There were no carcinogenic effects seen in females at the dosages tested. The exposure at the high dose was approximately 9-fold for the females that of the exposure in humans. There were no carcinogenic effects in rats. In this study, the exposure at the high dose was approximately 0.7-fold that of the exposure in humans with the 400/100 mg KALETRA twice daily regimen. Based on the exposures achieved in the animal studies, the significance of the observed effects is not known.

Mutagenesis

Neither lopinavir nor ritonavir was found to be mutagenic or clastogenic in a battery of in vitro and in vivo assays including the Ames bacterial reverse mutation assay using S. typhimurium and E. coli, the mouse lymphoma assay, the mouse micronucleus test and chromosomal aberration assays in human lymphocytes.

Impairment of Fertility

Lopinavir in combination with ritonavir at a 2:1 ratio produced no effects on fertility in male and female rats at levels of 10/5, 30/15 or 100/50 mg/kg/day. Based on AUC measurements, the exposures in rats at the high doses were approximately 0.7-fold for lopinavir and 1.8-fold for ritonavir of the exposures in humans at the recommended therapeutic dose (400/100 mg twice daily).

14 CLINICAL STUDIES

14.1 Adult Patients without Prior Antiretroviral Therapy

Study 863: KALETRA Capsules twice daily + stavudine + lamivudine compared to nelfinavir three times daily + stavudine + lamivudine

Study 863 was a randomized, double-blind, multicenter trial comparing treatment with KALETRA capsules (400/100 mg twice daily) plus stavudine and lamivudine versus nelfinavir (750 mg three times daily) plus stavudine and lamivudine in 653 antiretroviral treatment naïve patients. Patients had a mean age of 38 years (range: 19 to 84), 57% were Caucasian, and 80% were male. Mean baseline CD4+ cell count was 259 cells/mm^3 (range: 2 to 949 cells/mm^3) and mean baseline plasma HIV-1 RNA was 4.9 log10 copies/mL (range: 2.6 to 6.8 log10 copies/mL).

Treatment response and outcomes of randomized treatment are presented in Table 21.

Table 21. Outcomes of Randomized Treatment Through Week 48 (Study 863)

Outcome | KALETRA+d4T+3TC (N = 326) | Nelfinavir+d4T+3TC (N = 327)
Responder^1 | 75% | 62%
Virologic failure^2 Rebound Never suppressed through Week 48 | 9% 7% 2% | 25% 15% 9%
Death | 2% | 1%
Discontinued due to adverse events | 4% | 4%
Discontinued for other reasons^3 | 10% | 8%
1 Patients achieved and maintained confirmed HIV-1 RNA < 400 copies/mL through Week 48.
2 Includes confirmed viral rebound and failure to achieve confirmed < 400 copies/mL through Week 48.
3 Includes lost to follow-up, patient's withdrawal, non-compliance, protocol violation and other reasons. Overall discontinuation through Week 48, including patients who discontinued subsequent to virologic failure, was 17% in the KALETRA arm and 24% in the nelfinavir arm.

Through 48 weeks of therapy, there was a statistically significantly higher proportion of patients in the KALETRA arm compared to the nelfinavir arm with HIV-1 RNA < 400 copies/mL (75% vs. 62%, respectively) and HIV-1 RNA < 50 copies/mL (67% vs. 52%, respectively). Treatment response by baseline HIV-1 RNA level subgroups is presented in Table 22.

Table 22. Proportion of Responders Through Week 48 by Baseline Viral Load (Study 863)

Baseline Viral Load (HIV-1 RNA copies/mL) | KALETRA +d4T+3TC |  |  | Nelfinavir +d4T+3TC
 | <400 copies/mL ^1 | <50 copies/mL ^2 | n | <400 copies/mL ^1 | <50 copies/mL ^2 | n
< 30,000 | 74% | 71% | 82 | 79% | 72% | 87
≥ 30,000 to < 100,000 | 81% | 73% | 79 | 67% | 54% | 79
≥ 100,000 to < 250,000 | 75% | 64% | 83 | 60% | 47% | 72
≥ 250,000 | 72% | 60% | 82 | 44% | 33% | 89
1 Patients achieved and maintained confirmed HIV-1 RNA < 400 copies/mL through Week 48.
2 Patients achieved HIV-1 RNA < 50 copies/mL at Week 48.

Through 48 weeks of therapy, the mean increase from baseline in CD4+ cell count was 207 cells/mm^3 for the KALETRA arm and 195 cells/mm^3 for the nelfinavir arm.

Study 730: KALETRA Tablets once daily + tenofovir DF + emtricitabine compared to KALETRA Tablets twice daily + tenofovir DF + emtricitabine

Study 730 was a randomized, open-label, multicenter trial comparing treatment with KALETRA 800/200 mg once daily plus tenofovir DF and emtricitabine versus KALETRA 400/100 mg twice daily plus tenofovir DF and emtricitabine in 664 antiretroviral treatment-naïve patients. Patients were randomized in a 1:1 ratio to receive either KALETRA 800/200 mg once daily (n = 333) or KALETRA 400/100 mg twice daily (n = 331). Further stratification within each group was 1:1 (tablet vs. capsule). Patients administered the capsule were switched to the tablet formulation at Week 8 and maintained on their randomized dosing schedule. Patients were administered emtricitabine 200 mg once daily and tenofovir DF 300 mg once daily. Mean age of patients enrolled was 39 years (range: 19 to 71); 75% were Caucasian, and 78% were male. Mean baseline CD4+ cell count was 216 cells/mm^3 (range: 20 to 775 cells/mm^3) and mean baseline plasma HIV-1 RNA was 5.0 log10 copies/mL (range: 1.7 to 7.0 log10 copies/mL).

Treatment response and outcomes of randomized treatment through Week 48 are presented in Table 23.

Table 23. Outcomes of Randomized Treatment Through Week 48 (Study 730)

Outcome | KALETRA Once Daily + TDF + FTC (n = 333) | KALETRA Twice Daily + TDF + FTC (n = 331)
Responder^1 | 78% | 77%
Virologic failure^2 Rebound Never suppressed through Week 48 | 10% 5% 5% | 8% 5% 3%
Death | 1% | <1%
Discontinued due to adverse events | 4% | 3%
Discontinued for other reasons^3 | 8% | 11%
1 Patients achieved and maintained confirmed HIV-1 RNA < 50 copies/mL through Week 48.
2 Includes confirmed viral rebound and failure to achieve confirmed < 50 copies/mL through Week 48.
3 Includes lost to follow-up, patient's withdrawal, non-compliance, protocol violation and other reasons.

Through 48 weeks of therapy, 78% in the KALETRA once daily arm and 77% in the KALETRA twice daily arm achieved and maintained HIV-1 RNA < 50 copies/mL (95% confidence interval for the difference, -5.9% to 6.8%). Mean CD4+ cell count increases at Week 48 were 186 cells/mm^3 for the KALETRA once daily arm and 198 cells/mm^3 for the KALETRA twice daily arm.

14.2 Adult Patients with Prior Antiretroviral Therapy

Study 888: KALETRA Capsules twice daily + nevirapine + NRTIs compared to investigator-selected protease inhibitor(s) + nevirapine + NRTIs

Study 888 was a randomized, open-label, multicenter trial comparing treatment with KALETRA capsules (400/100 mg twice daily) plus nevirapine and nucleoside reverse transcriptase inhibitors versus investigator-selected protease inhibitor(s) plus nevirapine and nucleoside reverse transcriptase inhibitors in 288 single protease inhibitor-experienced, non-nucleoside reverse transcriptase inhibitor (NNRTI)-naïve patients. Patients had a mean age of 40 years (range: 18 to 74), 68% were Caucasian, and 86% were male. Mean baseline CD4+ cell count was 322 cells/mm^3 (range: 10 to 1059 cells/mm^3) and mean baseline plasma HIV-1 RNA was 4.1 log10 copies/mL (range: 2.6 to 6.0 log10 copies/mL).

Treatment response and outcomes of randomized treatment through Week 48 are presented in Table 24.

Table 24. Outcomes of Randomized Treatment Through Week 48 (Study 888)

Outcome | KALETRA + nevirapine + NRTIs (n = 148) | Investigator-Selected Protease Inhibitor(s) + nevirapine + NRTIs (n = 140)
Responder^1 | 57% | 33%
Virologic failure^2 Rebound Never suppressed through Week 48 | 24% 11% 13% | 41% 19% 23%
Death | 1% | 2%
Discontinued due to adverse events | 5% | 11%
Discontinued for other reasons^3 | 14% | 13%
1 Patients achieved and maintained confirmed HIV-1 RNA < 400 copies/mL through Week 48.
2 Includes confirmed viral rebound and failure to achieve confirmed < 400 copies/mL through Week 48.
3 Includes lost to follow-up, patient's withdrawal, non-compliance, protocol violation and other reasons.

Through 48 weeks of therapy, there was a statistically significantly higher proportion of patients in the KALETRA arm compared to the investigator-selected protease inhibitor(s) arm with HIV-1 RNA < 400 copies/mL (57% vs. 33%, respectively).

Through 48 weeks of therapy, the mean increase from baseline in CD4+ cell count was 111 cells/mm^3 for the KALETRA arm and 112 cells/mm^3 for the investigator-selected protease inhibitor(s) arm.

Study 802: KALETRA Tablets 800/200 mg Once Daily Versus 400/100 mg Twice Daily when Co-administered with Nucleoside/Nucleotide Reverse Transcriptase Inhibitors in Antiretroviral-Experienced, HIV-1 Infected Subjects

M06-802 was a randomized open-label study comparing the safety, tolerability, and antiviral activity of once daily and twice daily dosing of KALETRA tablets in 599 subjects with detectable viral loads while receiving their current antiviral therapy. Of the enrolled subjects, 55% on both treatment arms had not been previously treated with a protease inhibitor and 81 – 88% had received prior NNRTIs as part of their anti-HIV treatment regimen. Patients were randomized in a 1:1 ratio to receive either KALETRA 800/200 mg once daily (n = 300) or KALETRA 400/100 mg twice daily (n = 299). Patients were administered at least two nucleoside/nucleotide reverse transcriptase inhibitors selected by the investigator. Mean age of patients enrolled was 41 years (range: 21 to 73); 51% were Caucasian, and 66% were male. Mean baseline CD4+ cell count was 254 cells/mm^3 (range: 4 to 952 cells/mm^3) and mean baseline plasma HIV-1 RNA was 4.3 log10 copies/mL (range: 1.7 to 6.6 log10 copies/mL).

Treatment response and outcomes of randomized treatment through Week 48 are presented in Table 25.

Table 25. Outcomes of Randomized Treatment Through Week 48 (Study 802)

Outcome | KALETRA Once Daily + NRTIs (n = 300) | KALETRA Twice Daily + NRTIs (n = 299)
Virologic Success (HIV-1 RNA <50 copies/mL) | 57% | 54%
Virologic failure^1 | 22% | 24%
No virologic data in Week 48 window
Discontinued study due to adverse event or death^2 | 5% | 7%
Discontinued study for other reasons^3 | 13% | 12%
Missing data during window but on study | 3% | 3%
1 Includes patients who discontinued prior to Week 48 for lack or loss of efficacy and patients with HIV-1 RNA ≥ 50 copies/mL at Week 48.
2 Includes patients who discontinued due to adverse events or death at any time from Day 1 through Week 48 if this resulted in no virologic data on treatment at Week 48.
3 Includes withdrawal of consent, loss to follow-up, non-compliance, protocol violation and other reasons.

Through 48 weeks of treatment, the mean change from baseline for CD4 + cell count was 135 cells/mm^3 for the once daily group and 122 cells/mm^3 for the twice daily group.

14.3 Other Studies Supporting Approval in Adult Patients

Study 720: KALETRA twice daily + stavudine + lamivudine

Study 765: KALETRA twice daily + nevirapine + NRTIs

Study 720 (patients without prior antiretroviral therapy) and study 765 (patients with prior protease inhibitor therapy) were randomized, blinded, multi-center trials evaluating treatment with KALETRA at up to three dose levels (200/100 mg twice daily [720 only], 400/100 mg twice daily, and 400/200 mg twice daily). In Study 720, all patients switched to 400/100 mg twice daily between Weeks 48-72. Patients in study 720 had a mean age of 35 years, 70% were Caucasian, and 96% were male, while patients in study 765 had a mean age of 40 years, 73% were Caucasian, and 90% were male. Mean (range) baseline CD4+ cell counts for patients in study 720 and study 765 were 338 (3-918) and 372 (72-807) cells/mm^3, respectively. Mean (range) baseline plasma HIV-1 RNA levels for patients in study 720 and study 765 were 4.9 (3.3 to 6.3) and 4.0 (2.9 to 5.8) log10 copies/mL, respectively.

Through 360 weeks of treatment in study 720, the proportion of patients with HIV-1 RNA < 400 (< 50) copies/mL was 61% (59%) [n = 100]. Among patients completing 360 weeks of treatment with CD4+ cell count measurements [n=60], the mean (median) increase in CD4+ cell count was 501 (457) cells/mm^3. Thirty-nine patients (39%) discontinued the study, including 13 (13%) discontinuations due to adverse reactions and 1 (1%) death.

Through 144 weeks of treatment in study 765, the proportion of patients with HIV-1 RNA < 400 (< 50) copies/mL was 54% (50%) [n = 70], and the corresponding mean increase in CD4+ cell count was 212 cells/mm^3. Twenty-seven patients (39%) discontinued the study, including 5 (7%) discontinuations secondary to adverse reactions and 2 (3%) deaths.

14.4 Pediatric Studies

Study 1030 was an open-label, multicenter, dose-finding trial evaluating the pharmacokinetic profile, tolerability, safety and efficacy of KALETRA oral solution containing lopinavir 80 mg/mL and ritonavir 20 mg/mL at a dose of 300/75 mg/m^2 twice daily plus 2 NRTIs in HIV-1 infected infants ≥14 days and <6 months of age.

Ten infants, ≥14 days and <6 wks of age, were enrolled at a median (range) age of 5.7 (3.6-6.0) weeks and all completed 24 weeks. At entry, median (range) HIV-1 RNA was 6.0 (4.7-7.2) log10 copies/mL. Seven of 10 infants had HIV-1 RNA <400 copies/mL at Week 24. At entry, median (range) CD4+ percentage was 41 (16-59) with a median decrease of 1% (95% CI: -10, 18) from baseline to week 24 in 6 infants with available data.

Twenty-one infants, between 6 weeks and 6 months of age, were enrolled at a median (range) age of 14.7 (6.9-25.7) weeks and 19 of 21 infants completed 24 weeks. At entry, median (range) HIV RNA level was 5.8 (3.7-6.9) log10 copies/mL. Ten of 21 infants had HIV RNA <400 copies/mL at Week 24. At entry, the median (range) CD4+ percentage was 32 (11-54) with a median increase of 4% (95% CI: -1, 9) from baseline to week 24 in 19 infants with available data [see Clinical Pharmacology (12.3) for pharmacokinetic results].

Study 940 was an open-label, multicenter trial evaluating the pharmacokinetic profile, tolerability, safety and efficacy of KALETRA oral solution containing lopinavir 80 mg/mL and ritonavir 20 mg/mL in 100 antiretroviral naïve (44%) and experienced (56%) pediatric patients. All patients were non-nucleoside reverse transcriptase inhibitor naïve. Patients were randomized to either 230 mg lopinavir/57.5 mg ritonavir per m^2 or 300 mg lopinavir/75 mg ritonavir per m^2. Naïve patients also received lamivudine and stavudine. Experienced patients received nevirapine plus up to two nucleoside reverse transcriptase inhibitors.

Safety, efficacy and pharmacokinetic profiles of the two dose regimens were assessed after three weeks of therapy in each patient. After analysis of these data, all patients were continued on the 300 mg lopinavir/75 mg ritonavir per m^2 dose. Patients had a mean age of 5 years (range 6 months to 12 years) with 14% less than 2 years. Mean baseline CD4+ cell count was 838 cells/mm^3 and mean baseline plasma HIV-1 RNA was 4.7 log10 copies/mL.

Through 48 weeks of therapy, the proportion of patients who achieved and sustained an HIV-1 RNA < 400 copies/mL was 80% for antiretroviral naïve patients and 71% for antiretroviral experienced patients. The mean increase from baseline in CD4+ cell count was 404 cells/mm^3 for antiretroviral naïve and 284 cells/mm^3 for antiretroviral experienced patients treated through 48 weeks. At 48 weeks, two patients (2%) had prematurely discontinued the study. One antiretroviral naïve patient prematurely discontinued secondary to an adverse reaction, while one antiretroviral experienced patient prematurely discontinued secondary to an HIV-1 related event.

Dose selection in pediatric patients was based on the following:

- Among patients 14 days to 6 months of age receiving 300/75 mg/m^2 twice daily without nevirapine, plasma concentrations were lower than those observed in adults or in older children. This dose resulted in HIV-1 RNA < 400 copies/mL in 55% of patients (70% in those initiating treatment at <6 weeks of age).
- Among patients 6 months to 12 years of age, the 230/57.5 mg/m^2 oral solution twice daily regimen without nevirapine and the 300/75 mg/m^2 oral solution twice daily regimen with nevirapine provided lopinavir plasma concentrations similar to those obtained in adult patients receiving the 400/100 mg twice daily regimen (without nevirapine). These doses resulted in treatment benefit (proportion of patients with HIV-1 RNA < 400 copies/mL) similar to that seen in the adult clinical trials.
- Among patients 12 to 18 years of age receiving 400/100 mg/m^2 or 480/120 mg/m^2 (with efavirenz) twice daily, plasma concentrations were 60-100% higher than among 6 to 12 year old patients receiving 230/57.5 mg/m^2. Mean apparent clearance was similar to that observed in adult patients receiving standard dose and in patients 6 to 12 years of age. Although changes in HIV-1 RNA in patients with prior treatment failure were less than anticipated, the pharmacokinetic data supports use of similar dosing as in patients 6 to 12 years of age, not to exceed the recommended adult dose.
- For all age groups, the body surface area dosing was converted to body weight dosing using the patient’s prescribed lopinavir dose.

16 HOW SUPPLIED/STORAGE AND HANDLING

KALETRA® (lopinavir and ritonavir) tablets and oral solution are available in the following strengths and package sizes:

Formulation and strength | Available Presentations | Bottle size and NDC codes
Tablets: 200 mg lopinavir/ 50 mg ritonavir | Yellow film-coated ovaloid tablets debossed with the “a” logo and the code KA | Bottles of 120 tablets (NDC 0074-6799-22)
 | Red film-coated ovaloid tablets debossed with the code AL | Bottles of 120 tablets (NDC0074-4014-12)
Tablets: 100 mg lopinavir and 25 mg ritonavir | Pale yellow film-coated ovaloid tablets debossed with the “a” logo and the code KC | Bottles of 60 tablets (NDC 0074-0522-60)
 | Pink film-coated ovaloid tablets debossed with the code AC | Bottles of 60 tablets (NDC 0074-3008-60)
Oral Solution: 80 mg lopinavir and 20 mg ritonavir per mL | Light yellow to orange colored liquid supplied in amber-colored multiple-dose bottles containing 400 mg lopinavir and 100 mg ritonavir per 5 mL packaged with a marked dosing cup | 160 mL bottle (NDC 0074-3956-46)

Recommended Storage:

Tablets | Store KALETRA tablets at 20°- 25°C (68°- 77°F); excursions permitted to 15°- 30°C (59°- 86°F) [see USP controlled room temperature]. Dispense in original container or USP equivalent tight container. For patient use: exposure of this product to high humidity outside the original container or USP equivalent tight container for longer than 2 weeks is not recommended.
Oral Solution | Store KALETRA oral solution at 2°- 8°C (36°- 46°F) until dispensed. Avoid exposure to excessive heat. For patient use: refrigerated KALETRA oral solution remains stable until the expiration date printed on the label. If stored at room temperature up to 25°C (77°F), oral solution should be used within 2 months.

17 PATIENT COUNSELING INFORMATION

Advise the patient to read the FDA-approved patient labeling (Medication Guide)

General Administration Information [see Dosage and Administration (2)]:

- Advise patients to pay special attention to accurate administration of their dose to minimize the risk of accidental overdose or underdose of KALETRA.
- Advise patients and caregivers that the oral solution should be administered using the calibrated dosing cup (supplied) or oral dosing syringe.
- Advise caregivers to inform their healthcare provider if the child’s weight changes in order to make sure that the child’s KALETRA dose is adjusted as needed.
- Inform patients and caregivers that KALETRA tablets may be taken with or without food but KALETRA oral solution should be taken with food to enhance absorption.
- Advise patients to remain under the care of a healthcare provider while using KALETRA and to take KALETRA in combination with other antiretroviral drugs as prescribed.
- Advise patients not to alter the dose or discontinue therapy without consulting with their healthcare provider. If a dose of KALETRA is missed patients should take the dose as soon as possible and then return to their normal schedule. However, if a dose is skipped the patient should not double the next dose.
- Inform patients that it is important to take KALETRA on a regular dosing schedule as directed and to avoid missing doses as that can result in development of resistance.
- Inform patients that there may be a greater chance of developing diarrhea with the once daily regimen as compared with the twice daily regimen.
- Inform patients that Kaletra is not a cure for HIV-1 infection and that they may continue to experience illnesses associated with HIV-1 infection, including opportunistic infections.

Drug Interactions

Inform patients that KALETRA may interact with some drugs; therefore, patients should be advised to report to their healthcare provider the use of any prescription, non-prescription medication or herbal products such as St. John’s Wort [see Contraindications (4), Warnings and Precautions (5.1) and Drug Interactions (7)].

Pancreatitis

Advise patients that pancreatitis has been observed in patients receiving KALETRA and to alert their healthcare provider if they experience symptoms such as nausea, vomiting or abdominal pain [see Warnings and Precautions (5.3)].

Skin Rash

Inform patients that skin rash ranging in severity from mild to toxic epidermal necrolysis (TEN), Stevens-Johnson syndrome, erythema multiforme, urticaria, and angioedema have been reported in patients receiving KALETRA or its components lopinavir and/or ritonavir. Advise patients to contact their healthcare provider if they develop a rash while taking KALETRA [see Adverse Reactions (6.1)].

Hepatotoxicity

Pre-existing liver disease including Hepatitis B or C can worsen with use of KALETRA. This can be seen as worsening of transaminase elevations or hepatic decompensation. Advise patients that their liver function tests will need to be monitored closely especially during the first several months of KALETRA treatment and that they should notify their healthcare provider if they develop the signs and symptoms of worsening liver disease including loss of appetite, abdominal pain, jaundice, and itchy skin [see Warnings and Precautions (5.4)].

QT and PR Interval Prolongation

Advise patients that KALETRA may produce changes in the electrocardiogram (e.g., PR and/or QT prolongation) and to consult their healthcare provider if they experience symptoms such as dizziness, lightheadedness, abnormal heart rhythm or loss of consciousness [see Warnings and Precautions (5.5, 5.6)].

Diabetes Mellitus/Hyperglycemia

Advise patients that new onset of diabetes or exacerbation of pre-existing diabetes mellitus, and hyperglycemia have been reported during KALETRA use. Advise patients to notify their healthcare provider if they develop the signs and symptoms of diabetes mellitus including frequent urination, excessive thirst, extreme hunger or unusual weight loss and/or an increased blood sugar while on KALETRA as they may require a change in their diabetes treatment or new treatment [see Warnings and Precautions (5.7)].

Immune Reconstitution Syndrome

Advise patients that immune reconstitution syndrome has been reported in HIV-infected patients treated with combination antiretroviral therapy, including KALETRA [see Warnings and Precautions (5.8)].

Lipid Disorders

Advise patients that treatment with KALETRA therapy can result in substantial increases in the concentration of total cholesterol and triglycerides [see Warnings and Precautions (5.9)].

Fat Redistribution

Advise patients that redistribution or accumulation of body fat may occur in patients receiving antiretroviral therapy and that the cause and long term health effects of these conditions are not known at this time [see Warnings and Precautions (5.10)].

Patients with Hemophilia

Advise patients with hemophilia that they may experience increased bleeding when treated with protease inhibitors such as KALETRA [see Warnings and Precautions (5.11)].

Pregnancy Exposure Registry

Inform patients that there is an antiretroviral pregnancy registry that monitors fetal outcomes of pregnant women exposed to KALETRA [see Use in Specific Populations (8.1)].

Lactation

Instruct women with HIV-1 infection not to breastfeed because HIV-1 can be passed to the baby in breast milk [see Use in Specific Populations (8.2)].

Manufactured by AbbVie Inc., North Chicago, IL 60064 USA

KALETRA is a trademark of AbbVie Inc.

The brands listed are trademarks of their respective owners and are not trademarks of AbbVie Inc. The makers of these brands are not affiliated with and do not endorse AbbVie Inc. or its products.

© 2023 AbbVie Inc. All rights reserved.

20077914

MEDICATION GUIDE

KALETRA® (kuh-LEE-tra)
(lopinavir and ritonavir)
tablets

KALETRA® (kuh-LEE-tra)
(lopinavir and ritonavir)
oral solution

What is the most important information I should know about KALETRA?
KALETRA may cause serious side effects, including:

- Interactions with other medicines. It is important to know the medicines that should not be taken with KALETRA. For more information, see "Who should not take KALETRA?”
- Side Effects in babies taking KALETRA oral solution. KALETRA oral solution contains alcohol (ethanol) and propylene glycol. Call your healthcare provider right away if your baby appears too sleepy or their breathing changes.
- Inflammation of your pancreas (pancreatitis). KALETRA can cause pancreatitis which may be serious and may lead to death. People who have high levels of a certain fat (triglycerides) have a risk for developing pancreatitis. If you have advanced HIV-1 disease, you may have an increased risk of high triglyceride levels in your blood, and pancreatitis. If you have a history of pancreatitis, you may have an increased risk of it coming back again during treatment with KALETRA. Tell your healthcare provider if you have any signs or symptoms of pancreatitis including:

° nausea ° vomiting ° stomach-area (abdominal) pain

- Liver problems. Liver problems, including death, can happen in people who take KALETRA. Your healthcare provider should do blood tests before and during your treatment with KALETRA to check your liver function. If you have Hepatitis B or Hepatitis C, or other liver problems, you may have an increased risk for developing new or worsening of liver problems during treatment with KALETRA. Tell your healthcare provider right away if you have any signs and symptoms of liver problems including:

○ loss of appetite
○ yellow skin and whites of eyes (jaundice)
○ dark-colored urine

○ pale colored stools
○ itchy skin
○ stomach area (abdominal) pain

- Changes in your heart rhythm and the electrical activity of your heart. These changes may be seen on an EKG (electrocardiogram) and can lead to serious heart problems. Your risk for these problems may be higher if you:

○ have a history of abnormal heart rhythm or certain types of heart problems.
○ take other medicines that can affect your heart rhythm during treatment with KALETRA.
Tell your healthcare provider right away if you have any of these symptoms:

○ dizziness
○ lightheadedness

○ fainting
○ sensation of abnormal heartbeats

See “What are the possible side effects of KALETRA?” for more information about serious side effects.

What is KALETRA?
KALETRA is a prescription medicine that is used with other antiretroviral medicines to treat Human Immunodeficiency Virus-1 (HIV-1) infection in adults and children 14 days of age and older.
HIV is the virus that causes AIDS (Acquired Immune Deficiency Syndrome).
It is not known if KALETRA is safe and effective in children under 14 days old.

Who should not take KALETRA?
Do not take KALETRA if you:

- are allergic to lopinavir, ritonavir, or any of the ingredients in KALETRA. See the end of this Medication Guide for a complete list of ingredients in KALETRA.
- if you take any of the following medicines:
  ○ alfuzosin
  ○ apalutamide
  ○ ranolazine
  ○ dronedarone
  ○ colchicine, if you have kidney or liver problems.
  ○ rifampin
  ○ lurasidone
  ○ pimozide
  ○ ergot containing medicines including:

▪ dihydroergotamine mesylate
▪ ergotamine tartrate
▪ methylergonovine
○ cisapride
○ elbasvir/grazoprevir
○ lovastatin
○ simvastatin
○ lomitapide
○ sildenafil (Revatio®), when used for the treatment of pulmonary arterial hypertension
○ triazolam
○ midazolam when taken by mouth
○ St. John’s Wort (Hypericum perforatum®)
Serious problems can happen if you or your child takes any of the medicines listed above with KALETRA.

Before taking KALETRA, tell your healthcare provider about all of your medical conditions, including if you:

- have ever had a serious skin rash or an allergic reaction to medicines that contain lopinavir or ritonavir.
- have or had pancreas problems.
- have liver problems, including Hepatitis B or Hepatitis C.
- have any heart problems, including if you have a condition called Congenital Long QT Syndrome.
- have low potassium in your blood.
- have diabetes.
- have high cholesterol in your blood.
- have hemophilia. KALETRA may cause increased bleeding.
- are pregnant or plan to become pregnant. It is not known if KALETRA will harm your unborn baby.
  ○ KALETRA oral solution contains alcohol (ethanol) and propylene glycol. You should not take KALETRA oral solution during pregnancy because there is no safe level of alcohol exposure during pregnancy. Tell your healthcare provider if you become pregnant during treatment with KALETRA.
  ○ KALETRA may reduce how well hormonal birth control works. Females who may become pregnant should use another effective form of birth control or an additional barrier method of birth control during treatment with KALETRA.
  ○ Pregnancy Registry: There is a pregnancy registry for women who take antiretroviral medicines during pregnancy. The purpose of the pregnancy registry is to collect information about the health of you and your baby. Talk to your healthcare provider about how you can take part in this registry.
- are breastfeeding or plan to breastfeed. Do not breastfeed if you take KALETRA.
  ○ You should not breastfeed if you have HIV-1 because of the risk of passing HIV-1 to your baby.
  ○ Talk to your healthcare provider about the best way to feed your baby.

Tell your healthcare provider about all the medicines you take, including prescription and over-the-counter medicines, vitamins, and herbal supplements. Many medicines interact with KALETRA.
Keep a list of your medicines to show your healthcare provider and pharmacist.
You can ask your healthcare provider or pharmacist for a list of medicines that interact with KALETRA.
Do not start taking a new medicine without telling your healthcare provider. Your healthcare provider can tell you if it is safe to take KALETRA with other medicines. Your healthcare provider may need to change the dose of other medicines during treatment with KALETRA.

How should I take KALETRA?

- Take KALETRA every day exactly as prescribed by your healthcare provider.
- Stay under the care of your healthcare provider during treatment with KALETRA.
- It is important to set up a dosing schedule and follow it every day.
- Do not change your treatment or stop treatment without first talking with your healthcare provider.
- Swallow KALETRA tablets whole. Do not chew, break, or crush KALETRA tablets.
- KALETRA tablets can be taken with or without food.
- KALETRA oral solution must be taken with food.
- If you are taking both didanosine and KALETRA:
  ○ Didanosine can be taken at the same time as KALETRA tablets, without food.
  ○ Take didanosine either 1 hour before or 2 hours after taking KALETRA oral solution.
- If you are pregnant:
  ○ You should not take KALETRA tablets on a 1 time each day dose schedule.
  ○ Avoid use of KALETRA oral solution.
- If your child is prescribed KALETRA:
  ○ Tell your healthcare provider if your child’s weight changes.
- KALETRA should not be given to children on a 1 time each day dose schedule. When giving KALETRA to your child, give KALETRA exactly as prescribed.
  ○ Use the dosing cup (supplied) or an oral syringe with mL (milliliter) markings to give the prescribed dose of KALETRA oral solution to your child. Your pharmacist should provide an oral syringe to you.
  ○ KALETRA oral solution contains propylene glycol and a large amount of alcohol (ethanol). KALETRA oral solution should not be given to babies younger than 14 days of age unless your healthcare provider thinks it is right for your baby.
- Talk with your healthcare provider if you plan to take or give KALETRA oral solution through a feeding tube. KALETRA oral solution contains propylene glycol and alcohol (ethanol), and should not be used with certain feeding tubes.
- You may have a greater chance of getting diarrhea if you take KALETRA 1 time each day than if you take it 2 times each day.
- Do not miss a dose of KALETRA. This could make the virus harder to treat. If you forget to take KALETRA, take the missed dose right away. If it is almost time for your next dose, do not take the missed dose. Instead, follow your regular dosing schedule by taking your next dose at its regular time. Do not take more than one dose of KALETRA at one time.
- If you or your child take more than the prescribed dose of KALETRA, call your healthcare provider or go to the nearest emergency room right away.

What are the possible side effects of KALETRA?
KALETRA can cause serious side effects, including:

- See “What is the most important information I should know about KALETRA?”

- Diabetes and high blood sugar (hyperglycemia). You may develop new or worsening diabetes or high blood sugar during treatment with KALETRA. Tell your healthcare provider if you get any of the following signs or symptoms:

○ urinate more often than usual
○ increased hunger or thirst

○ unusual weight loss
○ increase in your blood sugar levels

Your healthcare provider may need to start you on medicine to treat high blood sugar or change your diabetes medicines.

- Changes in your immune system (Immune Reconstitution Syndrome) can happen when you start taking HIV-1 medicines. Your immune system may get stronger and begin to fight infections that have been hidden in your body for a long time. Call your healthcare provider right away if you start having new symptoms after starting your HIV-1 medicine.
- Increases in certain fat (triglycerides and cholesterol) levels in your blood. Large increases of triglycerides and cholesterol can be seen in blood test results of some people who take KALETRA. Your healthcare provider should do blood tests to check your cholesterol and triglyceride levels before you start taking KALETRA and during your treatment.
- Changes in body fat can happen in some people who take antiretroviral therapy. These changes may include increased amount of fat in the upper back and neck ("buffalo hump"), breast, and around the middle of your body (trunk). Loss of fat from the legs, arms and face may also happen. The exact cause and long-term health effects of these conditions are not known at this time.
- Increased bleeding in people with hemophilia. Some people with hemophilia have increased bleeding with KALETRA or similar medicines.
- Skin rash, which can be severe, can happen in people who take KALETRA. Tell your healthcare provider if you have a history of skin rash with other medicine used to treat your HIV-1 infection or if you get any skin rash during treatment with KALETRA.
- Kidney stones

Common side effects of KALETRA include:

• diarrhea
• nausea

• vomiting
• increased fats in blood (triglycerides or cholesterol)

These are not all of the possible side effects of KALETRA. For more information, ask your healthcare provider or pharmacist.
Call your doctor for medical advice about side effects. You may report side effects to FDA at 1-800-FDA-1088.

How should I store KALETRA?
KALETRA tablets:

- Store KALETRA tablets at room temperature, between 68°F to 77°F (20°C to 25°C).
- Store KALETRA tablets in the original container.
- Do not keep KALETRA tablets out of the container it comes in for longer than 2 weeks, especially in areas where there is a lot of humidity.
- Keep the container closed tightly.

KALETRA oral solution:

- Store KALETRA oral solution in a refrigerator, between 36°F to 46°F (2°C to 8°C). KALETRA oral solution that is kept refrigerated may be used until the expiration date printed on the label.
- KALETRA oral solution that is stored at room temperature (less than 77°F or 25°C) should be used within 2 months.
- Keep KALETRA oral solution away from high heat.
- Throw away any medicine that is out of date or that you no longer need.

Keep KALETRA and all medicines out of the reach of children.

General information about the safe and effective use of KALETRA.
Medicines are sometimes prescribed for purposes other than those listed in a Medication Guide. Do not use KALETRA for a condition for which it was not prescribed. Do not give KALETRA to other people, even if they have the same condition you have. It may harm them.
You can ask your pharmacist or healthcare provider for information about KALETRA that is written for health professionals.

What are the ingredients in KALETRA?
Active ingredients: lopinavir and ritonavir
Inactive ingredients:
KALETRA 200 mg lopinavir and 50 mg ritonavir yellow tablets: colloidal silicon dioxide, copovidone, sodium stearyl fumarate, and sorbitan monolaurate. The film coating contains: colloidal silicone dioxide, hydroxypropyl cellulose, hypromellose, polyethylene glycol 400, polyethylene glycol 3350, polysorbate 80, talc, titanium dioxide, and yellow ferric oxide E172.
KALETRA 200 mg lopinavir and 50 mg ritonavir red tablets: colloidal silicon dioxide, copovidone, sodium stearyl fumarate, and sorbitan monolaurate. The film coating contains: colloidal silicone dioxide, hydroxypropyl cellulose, hypromellose, polyethylene glycol 400, polyethylene glycol 3350, polysorbate 80, talc, titanium dioxide, and red ferric oxide E172.
KALETRA 100 mg lopinavir and 25 mg ritonavir pale yellow tablets: colloidal silicon dioxide, copovidone, sodium stearyl fumarate, and sorbitan monolaurate. The film coating contains: polyethylene glycol 3350, polyvinyl alcohol, talc, titanium dioxide, and yellow ferric oxide E172.
KALETRA 100 mg lopinavir and 25 mg ritonavir pink tablets: colloidal silicon dioxide, copovidone, sodium stearyl fumarate, and sorbitan monolaurate. The film coating contains: polyethylene glycol 3350, polyvinyl alcohol, talc, titanium dioxide, and red ferric oxide E172.
KALETRA oral solution: acesulfame potassium, artificial cotton candy flavor, citric acid, ethanol (a type of alcohol), glycerin, high fructose corn syrup, Magnasweet-110 flavor, menthol, natural and artificial vanilla flavor, peppermint oil, polyoxyl 40 hydrogenated castor oil, povidone, propylene glycol, saccharin sodium, sodium chloride, sodium citrate, and water.
KALETRA oral solution contains approximately 42% ethanol (a type of alcohol) and approximately 15% propylene glycol. “See How should I take KALETRA?”
For more information about KALETRA call 1-800-633-9110 or go to www.KALETRA.com
Manufactured by AbbVie Inc., North Chicago, IL 60064 USA
KALETRA is a trademark of AbbVie Inc. © 2023 AbbVie Inc. All rights reserved.
The brands listed are trademarks of their respective owners and are not trademarks of AbbVie Inc. The makers of these brands are not affiliated with and do not endorse AbbVie Inc. or its products.
20077914

This Medication Guide has been approved by the U.S. Food and Drug Administration.
Revised: April 2023

PACKAGE LABEL

NDC 0074-6799-22

Kaletra®

(Lopinavir and Ritonavir)

Tablets

200 mg / 50 mg

120 Tablets

ALERT: Find out about medicines that should NOT be taken with Kaletra®

Attention Pharmacist: Do not cover ALERT box with pharmacy label.

Dispense the accompanying Medication Guide to each patient.

Rx only abbvie

PACKAGE LABEL

NDC 0074-2605-21

Kaletra®

(Lopinavir and Ritonavir)

Tablets

200 mg / 50 mg

120 Tablets

ALERT: Find out about medicines that should NOT be taken with Kaletra®

Attention Pharmacist: Do not cover ALERT box with pharmacy label.

Dispense the accompanying Medication Guide to each patient.

Rx only abbvie

PACKAGE LABEL

NDC 0074-0522-60

Kaletra®

(Lopinavir and Ritonavir)

Tablets

100 mg / 25 mg

60 Tablets

ALERT: Find out about medicines that should NOT be taken with Kaletra®

Attention Pharmacist: Do not cover ALERT box with pharmacy label.

Dispense the accompanying Medication Guide to each patient

Rx only abbvie

PACKAGE LABEL

NDC 0074-1575-21

Kaletra®

(Lopinavir and Ritonavir)

Tablets

100 mg / 25mg

60 Tablets

ALERT: Find out about medicines that should NOT be taken with Kaletra®

Attention Pharmacist: Do not cover ALERT box with pharmacy label.

Dispense the accompanying Medication Guide to each patient

Rx only abbvie

PACKAGE LABEL

NDC 0074-3956-46

Kaletra®

Lopinavir and Ritonavir Oral Solution

80 mg /20 mg per mL

160 mL

ALERT: Find out about medicines that should NOT be taken with KALETRA

Attention Pharmacist: Do not cover ALERT box or expiration date with pharmacy label. Store and dispense in original container.

Dispense the enclosed Medication Guide to each patient.

Rx only abbvie

PACKAGE LABEL

NDC 0074-4014-12

Kaletra®

(Lopinavir and Ritonavir)

Tablets

200 mg / 50 mg

ALERT: Find out about medicines that should NOT be taken with Kaletra®

Attention Pharmacist: Do not cover ALERT box with pharmacy label.

Dispense the accompanying Medication Guide to each patient.

Rx only abbvie

PACKAGE LABEL

NDC 0074-3008-60

Kaletra®

(Lopinavir and Ritonavir)

Tablets

100 mg / 25mg

60 Tablets

ALERT: Find out about medicines that should NOT be taken with Kaletra®

Attention Pharmacist: Do not cover ALERT box with pharmacy label.

Dispense the accompanying Medication Guide to each patient

Rx only abbvie